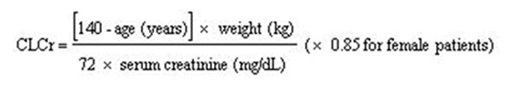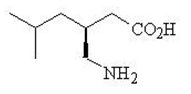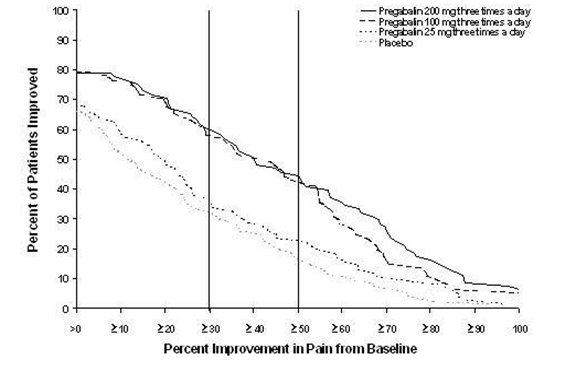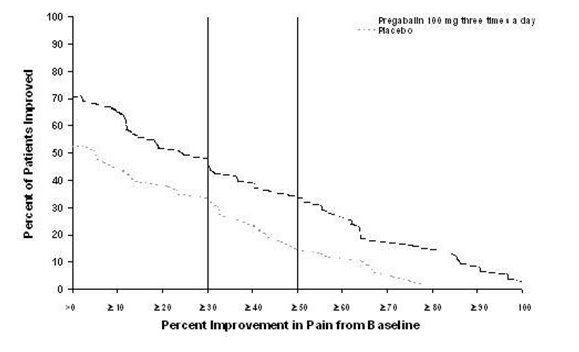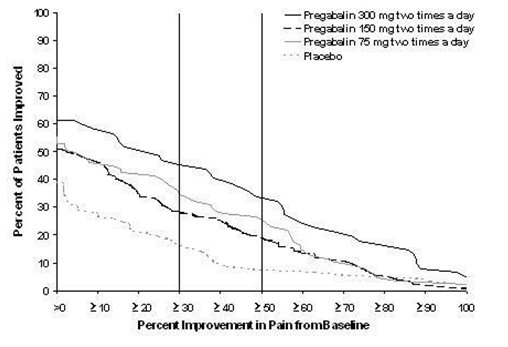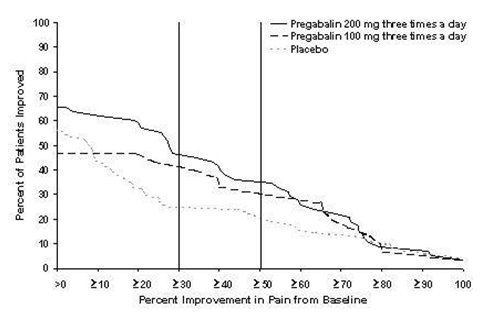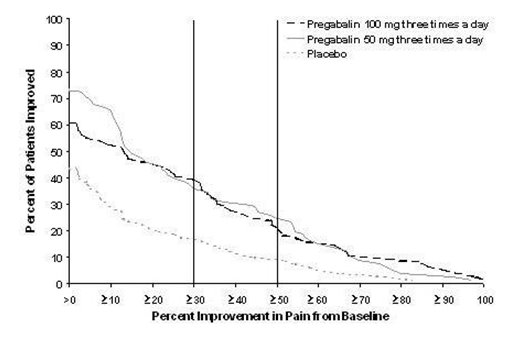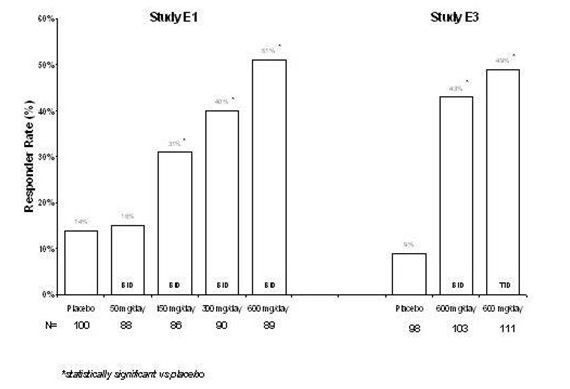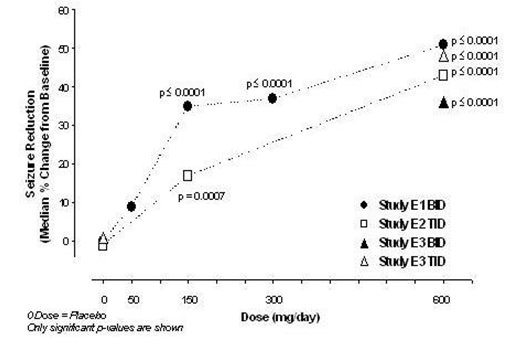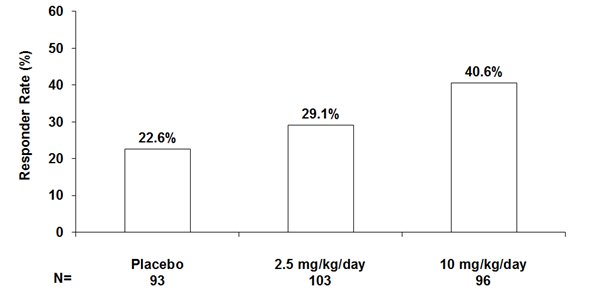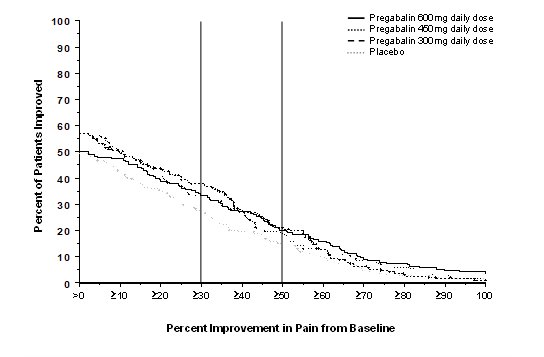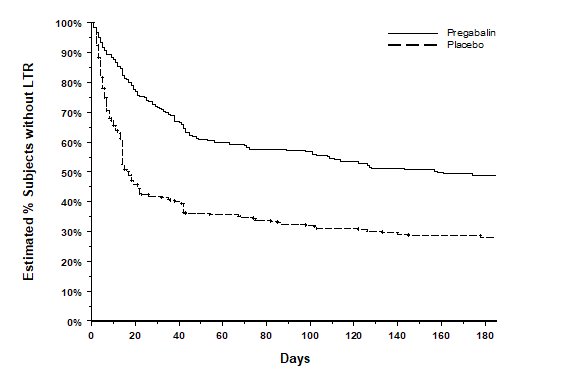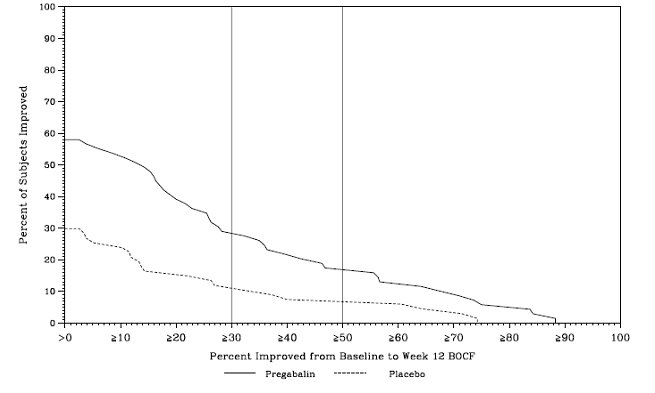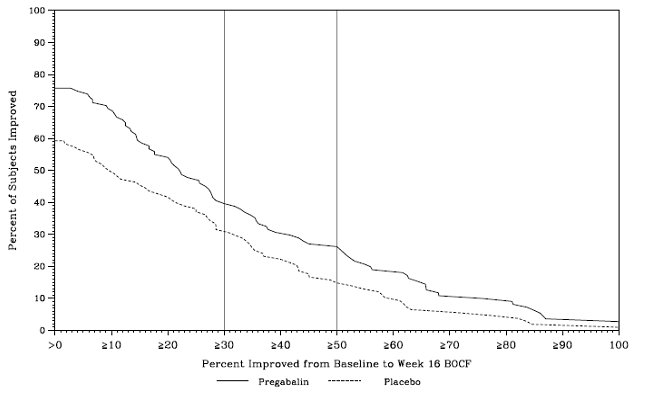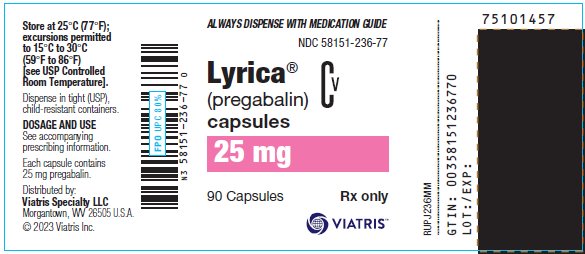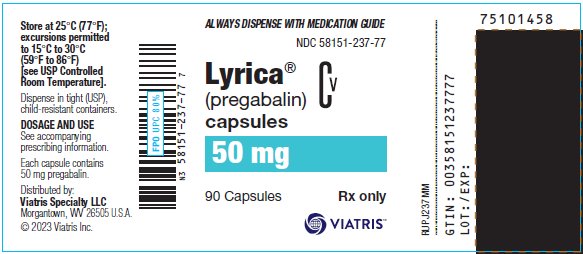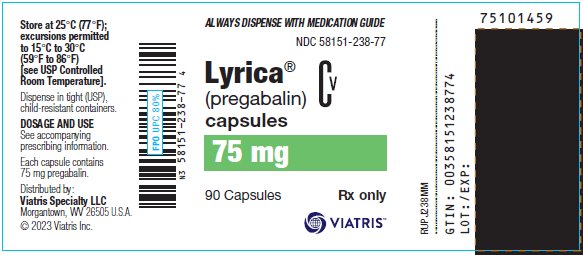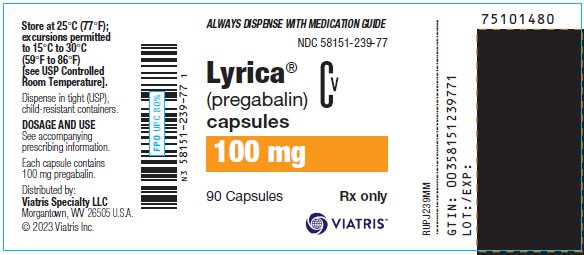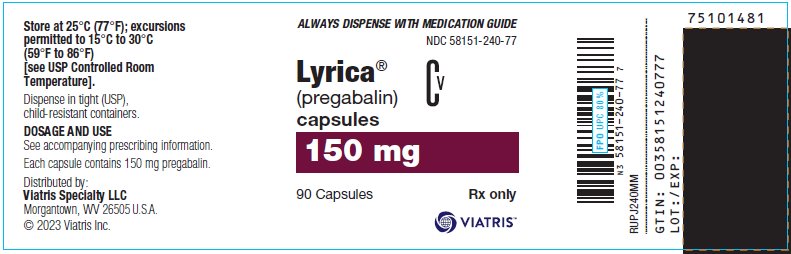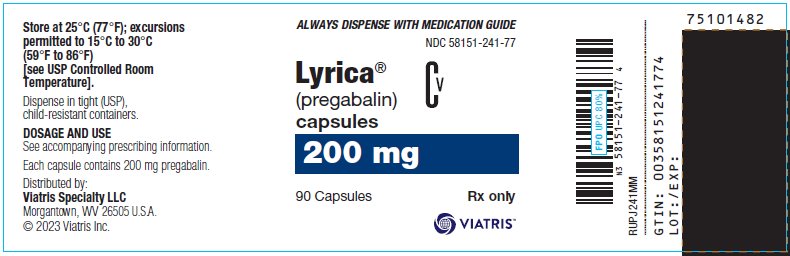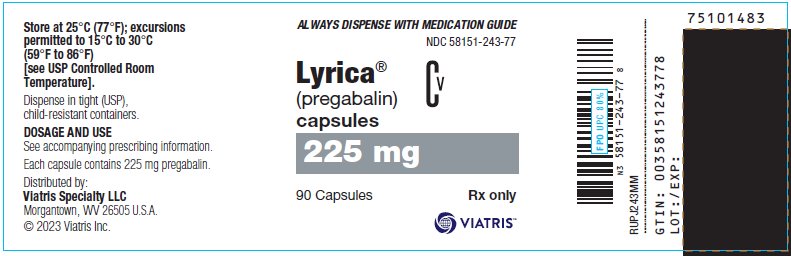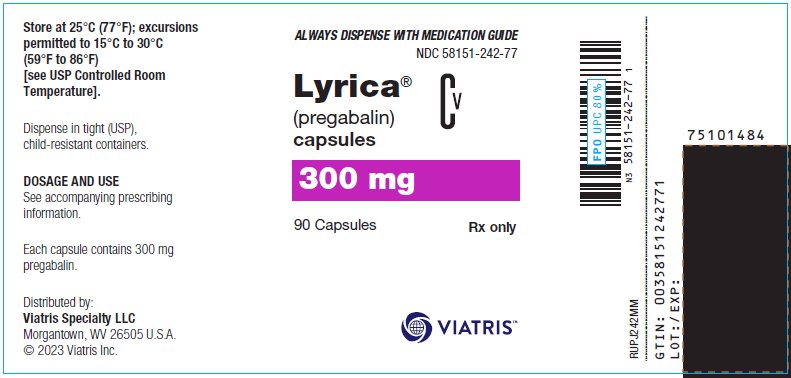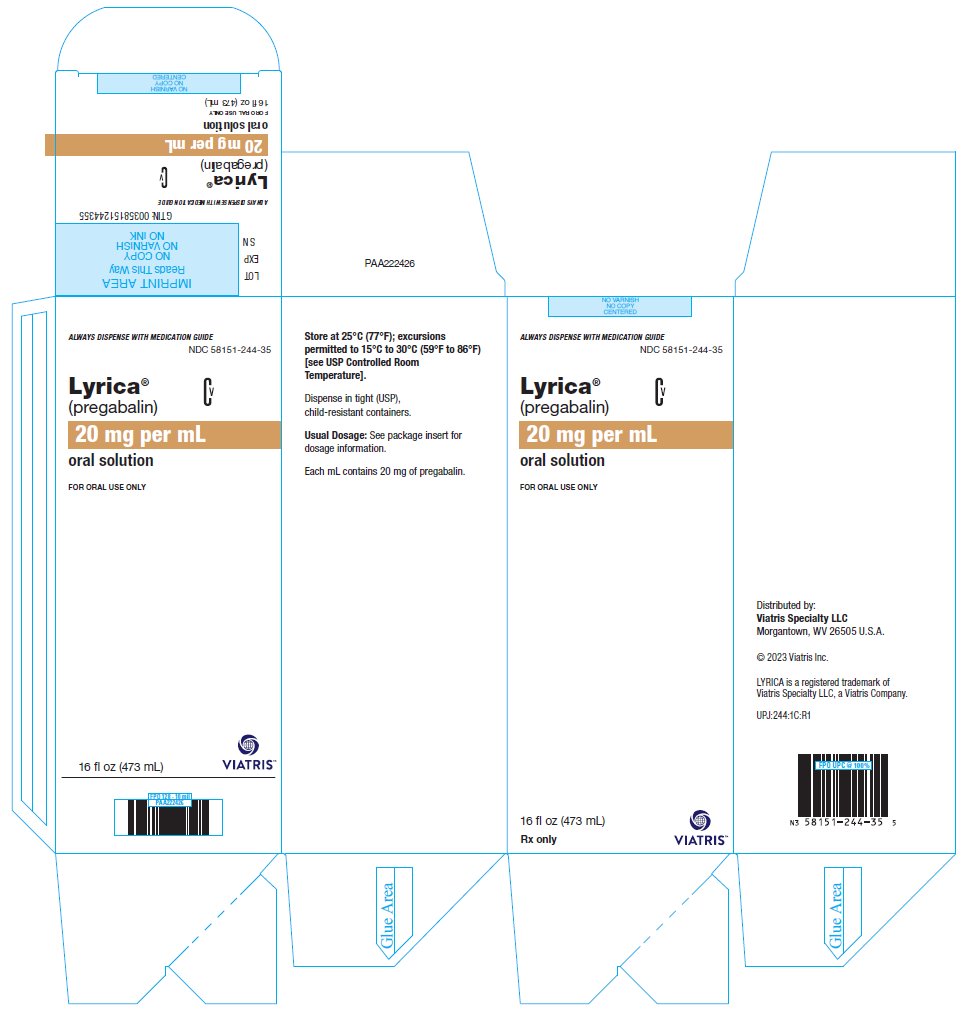 DRUG LABEL: Lyrica
NDC: 58151-236 | Form: CAPSULE
Manufacturer: Viatris Specialty LLC
Category: prescription | Type: HUMAN PRESCRIPTION DRUG LABEL
Date: 20250415
DEA Schedule: CV

ACTIVE INGREDIENTS: PREGABALIN 25 mg/1 1
INACTIVE INGREDIENTS: LACTOSE MONOHYDRATE; STARCH, CORN; TALC; GELATIN, UNSPECIFIED; TITANIUM DIOXIDE; SODIUM LAURYL SULFATE; SILICON DIOXIDE; SHELLAC; FERROSOFERRIC OXIDE; PROPYLENE GLYCOL; POTASSIUM HYDROXIDE

HIGHLIGHTS OF PRESCRIBING INFORMATION

These highlights do not include all the information needed to use LYRICA safely and effectively. See full prescribing information for LYRICA.
LYRICA (pregabalin) Capsules, CV
LYRICA (pregabalin) Oral Solution, CV
Initial U.S. Approval: 2004

RECENT MAJOR CHANGES

Warnings and Precautions (5.3, 5.4) 04/2025

1 INDICATIONS AND USAGE

LYRICA is indicated for:

- Neuropathic pain associated with diabetic peripheral neuropathy (DPN) (1)
- Postherpetic neuralgia (PHN) (1)
- Adjunctive therapy for the treatment of partial‑onset seizures in patients 1 month of age and older (1)
- Fibromyalgia (1)
- Neuropathic pain associated with spinal cord injury (1)

2 DOSAGE AND ADMINISTRATION

- For adult indications, begin dosing at 150 mg/day. For partial‑onset seizure dosing in pediatric patients 1 month of age and older, refer to section 2.4. (2.2, 2.3, 2.4, 2.5, 2.6)
- Dosing recommendations:

INDICATION | Dosing Regimen | Maximum Dose
DPN Pain (2.2) | 3 divided doses per day | 300 mg/day within 1 week.
PHN (2.3) | 2 or 3 divided doses per day | 300 mg/day within 1 week.; Maximum dose of 600 mg/day.
Adjunctive Therapy for Partial‑Onset Seizures in Pediatric and Adult Patients Weighing 30 kg or More (2.4) | 2 or 3 divided doses per day | Maximum dose of 600 mg/day.
Adjunctive Therapy for Partial‑Onset Seizures in Pediatric Patients Weighing Less than 30 kg (2.4) | 1 month to less than 4 years:; 3 divided doses per day; 4 years and older:; 2 or 3 divided doses per day | 14 mg/kg/day.
Fibromyalgia (2.5) | 2 divided doses per day | 300 mg/day within 1 week.; Maximum dose of 450 mg/day.
Neuropathic Pain Associated with Spinal Cord Injury (2.6) | 2 divided doses per day | 300 mg/day within 1 week.; Maximum dose of 600 mg/day.

- Dose should be adjusted in adult patients with reduced renal function. (2.7)

3 DOSAGE FORMS AND STRENGTHS

- Capsules: 25 mg, 50 mg, 75 mg, 100 mg, 150 mg, 200 mg, 225 mg, and 300 mg. (3)
- Oral Solution: 20 mg/mL. (3)

4 CONTRAINDICATIONS

- Known hypersensitivity to pregabalin or any of its components. (4)

5 WARNINGS AND PRECAUTIONS

- Angioedema (e.g., swelling of the throat, head, and neck) can occur, and may be associated with life-threatening respiratory compromise requiring emergency treatment. Discontinue LYRICA immediately in these cases. (5.1)
- Hypersensitivity reactions (e.g., hives, dyspnea, and wheezing) can occur. Discontinue LYRICA immediately in these patients. (5.2)
- Antiepileptic drugs, including pregabalin, the active ingredient in LYRICA, increase the risk of suicidal thoughts or behavior. (5.3)
- Abrupt or rapid discontinuation may increase the risk for seizures. Withdrawal symptoms or suicidal behavior and ideation have been observed after discontinuation. Taper LYRICA gradually over a minimum of 1 week. (5.4)
- Respiratory depression: May occur with LYRICA, when used with concomitant CNS depressants or in the setting of underlying respiratory impairment. Monitor patients and adjust dosage as appropriate. (5.5)
- LYRICA may cause dizziness and somnolence and impair patients’ ability to drive or operate machinery. (5.6)
- LYRICA may cause peripheral edema. Exercise caution when co-administering LYRICA and thiazolidinedione antidiabetic agents. (5.7)

6 ADVERSE REACTIONS

Most common adverse reactions (greater than or equal to 5% and twice placebo) in adults are dizziness, somnolence, dry mouth, edema, blurred vision, weight gain, and thinking abnormal (primarily difficulty with concentration/attention). (6.1)

Most common adverse reactions (greater than or equal to 5% and twice placebo) in pediatric patients for the treatment of partial‑onset seizures are increased weight and increased appetite. (6.1)

To report SUSPECTED ADVERSE REACTIONS, contact Viatris at 1-877-446-3679 (1-877-4-INFO-RX) or FDA at 1-800-FDA-1088 or www.fda.gov/medwatch.

8 USE IN SPECIFIC POPULATIONS

- Lactation: Breastfeeding is not recommended. (8.2)

FULL PRESCRIBING INFORMATION

1 INDICATIONS AND USAGE

LYRICA is indicated for:

- Management of neuropathic pain associated with diabetic peripheral neuropathy
- Management of postherpetic neuralgia
- Adjunctive therapy for the treatment of partial‑onset seizures in patients 1 month of age and older
- Management of fibromyalgia
- Management of neuropathic pain associated with spinal cord injury

2 DOSAGE AND ADMINISTRATION

2.1 Important Administration Instructions

LYRICA is given orally with or without food.

When discontinuing LYRICA, taper gradually over a minimum of 1 week [see Warnings and Precautions (5.4)].

Because LYRICA is eliminated primarily by renal excretion, adjust the dose in adult patients with reduced renal function [see Dosage and Administration (2.7)].

2.2 Neuropathic Pain Associated with Diabetic Peripheral Neuropathy in Adults

The maximum recommended dose of LYRICA is 100 mg three times a day (300 mg/day) in patients with creatinine clearance of at least 60 mL/min. Begin dosing at 50 mg three times a day (150 mg/day). The dose may be increased to 300 mg/day within 1 week based on efficacy and tolerability.

Although LYRICA was also studied at 600 mg/day, there is no evidence that this dose confers additional significant benefit and this dose was less well tolerated. In view of the dose-dependent adverse reactions, treatment with doses above 300 mg/day is not recommended [see Adverse Reactions (6.1)].

2.3 Postherpetic Neuralgia in Adults

The recommended dose of LYRICA is 75 to 150 mg two times a day, or 50 to 100 mg three times a day (150 to 300 mg/day) in patients with creatinine clearance of at least 60 mL/min. Begin dosing at 75 mg two times a day, or 50 mg three times a day (150 mg/day). The dose may be increased to 300 mg/day within 1 week based on efficacy and tolerability.

Patients who do not experience sufficient pain relief following 2 to 4 weeks of treatment with 300 mg/day, and who are able to tolerate LYRICA, may be treated with up to 300 mg two times a day, or 200 mg three times a day (600 mg/day). In view of the dose-dependent adverse reactions and the higher rate of treatment discontinuation due to adverse reactions, reserve dosing above 300 mg/day for those patients who have on-going pain and are tolerating 300 mg daily [see Adverse Reactions (6.1)].

2.4 Adjunctive Therapy for Partial-Onset Seizures in Patients 1 Month of Age and Older

The recommended dosages for adults and pediatric patients 1 month of age and older are included in Table 1. Administer the total daily dosage orally in two or three divided doses as indicated in Table 1. In pediatric patients, the recommended dosing regimen is dependent upon body weight. Based on clinical response and tolerability, dosage may be increased, approximately weekly.

Table 1. Recommended Dosage for Adults and Pediatric Patients 1 Month and Older
Age and Body Weight | Recommended Initial Dosage | Recommended Maximum Dosage | Frequency of Administration
Adults (17 years and older) | 150 mg/day | 600 mg/day | 2 or 3 divided doses
Pediatric patients weighing 30 kg or more | 2.5 mg/kg/day | 10 mg/kg/day (not to exceed 600 mg/day) | 2 or 3 divided doses
Pediatric patients weighing less than 30 kg | 3.5 mg/kg/day | 14 mg/kg/day | 1 month to less than 4 years of age: 3 divided doses; 4 years of age and older: 2 or 3 divided doses

Both the efficacy and adverse event profiles of LYRICA have been shown to be dose-related.

The effect of dose escalation rate on the tolerability of LYRICA has not been formally studied.

The efficacy of adjunctive LYRICA in patients taking gabapentin has not been evaluated in controlled trials. Consequently, dosing recommendations for the use of LYRICA with gabapentin cannot be offered.

2.5 Management of Fibromyalgia in Adults

The recommended dose of LYRICA for fibromyalgia is 300 to 450 mg/day. Begin dosing at 75 mg two times a day (150 mg/day). The dose may be increased to 150 mg two times a day (300 mg/day) within 1 week based on efficacy and tolerability. Patients who do not experience sufficient benefit with 300 mg/day may be further increased to 225 mg two times a day (450 mg/day). Although LYRICA was also studied at 600 mg/day, there is no evidence that this dose confers additional benefit and this dose was less well tolerated. In view of the dose‑dependent adverse reactions, treatment with doses above 450 mg/day is not recommended [see Adverse Reactions (6.1)].

2.6 Neuropathic Pain Associated with Spinal Cord Injury in Adults

The recommended dose range of LYRICA for the treatment of neuropathic pain associated with spinal cord injury is 150 to 600 mg/day. The recommended starting dose is 75 mg two times a day (150 mg/day). The dose may be increased to 150 mg two times a day (300 mg/day) within 1 week based on efficacy and tolerability. Patients who do not experience sufficient pain relief after 2 to 3 weeks of treatment with 150 mg two times a day and who tolerate LYRICA may be treated with up to 300 mg two times a day [see Clinical Studies (14.5)].

2.7 Dosing for Adult Patients with Renal Impairment

In view of dose-dependent adverse reactions and since LYRICA is eliminated primarily by renal excretion, adjust the dose in adult patients with reduced renal function. The use of LYRICA in pediatric patients with compromised renal function has not been studied.

Base the dose adjustment in patients with renal impairment on creatinine clearance (CLcr), as indicated in Table 2. To use this dosing table, an estimate of the patient’s CLcr in mL/min is needed. CLcr in mL/min may be estimated from serum creatinine (mg/dL) determination using the Cockcroft and Gault equation:

Next, refer to the Dosage and Administration section to determine the recommended total daily dose based on indication, for a patient with normal renal function (CLcr greater than or equal to 60 mL/min). Then refer to Table 2 to determine the corresponding renal adjusted dose.

(For example: A patient initiating LYRICA therapy for postherpetic neuralgia with normal renal function (CLcr greater than or equal to 60 mL/min), receives a total daily dose of 150 mg/day pregabalin. Therefore, a renal impaired patient with a CLcr of 50 mL/min would receive a total daily dose of 75 mg/day pregabalin administered in two or three divided doses.)

For patients undergoing hemodialysis, adjust the pregabalin daily dose based on renal function. In addition to the daily dose adjustment, administer a supplemental dose immediately following every 4-hour hemodialysis treatment (see Table 2).

Table 2. Pregabalin Dosage Adjustment Based on Renal Function
Creatinine Clearance (CLcr) (mL/min) | Total Pregabalin Daily Dose; (mg/day) [Total daily dose (mg/day) should be divided as indicated by dose regimen to provide mg/dose.] |  |  |  | Dose Regimen
Greater than or equal to 60 | 150 | 300 | 450 | 600 | BID or TID
30-60 | 75 | 150 | 225 | 300 | BID or TID
15-30 | 25-50 | 75 | 100-150 | 150 | QD or BID
Less than 15 | 25 | 25-50 | 50-75 | 75 | QD
Supplementary dosage following hemodialysis (mg) [Supplementary dose is a single additional dose.]
Patients on the 25 mg QD regimen: take one supplemental dose of 25 mg or 50 mg
Patients on the 25-50 mg QD regimen: take one supplemental dose of 50 mg or 75 mg
Patients on the 50-75 mg QD regimen: take one supplemental dose of 75 mg or 100 mg
Patients on the 75 mg QD regimen: take one supplemental dose of 100 mg or 150 mg
TID = Three divided doses; BID = Two divided doses; QD = Single daily dose.

3 DOSAGE FORMS AND STRENGTHS

Capsules: 25 mg, 50 mg, 75 mg, 100 mg, 150 mg, 200 mg, 225 mg, and 300 mg
Oral Solution: 20 mg/mL

[see Description (11) and How Supplied/Storage and Handling (16)]

4 CONTRAINDICATIONS

LYRICA is contraindicated in patients with known hypersensitivity to pregabalin or any of its components. Angioedema and hypersensitivity reactions have occurred in patients receiving pregabalin therapy [see Warnings and Precautions (5.2)].

5 WARNINGS AND PRECAUTIONS

5.1 Angioedema

There have been postmarketing reports of angioedema in patients during initial and chronic treatment with LYRICA. Specific symptoms included swelling of the face, mouth (tongue, lips, and gums), and neck (throat and larynx). There were reports of life-threatening angioedema with respiratory compromise requiring emergency treatment. Discontinue LYRICA immediately in patients with these symptoms.

Exercise caution when prescribing LYRICA to patients who have had a previous episode of angioedema. In addition, patients who are taking other drugs associated with angioedema (e.g., angiotensin converting enzyme inhibitors [ACE-inhibitors]) may be at increased risk of developing angioedema.

5.2 Hypersensitivity

There have been postmarketing reports of hypersensitivity in patients shortly after initiation of treatment with LYRICA. Adverse reactions included skin redness, blisters, hives, rash, dyspnea, and wheezing. Discontinue LYRICA immediately in patients with these symptoms.

5.3 Suicidal Behavior and Ideation

Antiepileptic drugs (AEDs), including pregabalin, the active ingredient in LYRICA, increase the risk of suicidal thoughts or behavior in patients taking these drugs for any indication. Suicidal behavior and ideation have also been reported in patients after discontinuation of pregabalin [see Warnings and Precautions (5.4)]. Monitor patients treated with any AED for any indication for the emergence or worsening of depression, suicidal thoughts or behavior, and/or any unusual changes in mood or behavior.

Pooled analyses of 199 placebo-controlled clinical trials (mono- and adjunctive therapy) of 11 different AEDs showed that patients randomized to one of the AEDs had approximately twice the risk (adjusted Relative Risk 1.8, 95% CI:1.2, 2.7) of suicidal thinking or behavior compared to patients randomized to placebo. In these trials, which had a median treatment duration of 12 weeks, the estimated incidence rate of suicidal behavior or ideation among 27,863 AED‑treated patients was 0.43%, compared to 0.24% among 16,029 placebo-treated patients, representing an increase of approximately one case of suicidal thinking or behavior for every 530 patients treated. There were four suicides in drug-treated patients in the trials and none in placebo-treated patients, but the number is too small to allow any conclusion about drug effect on suicide.

The increased risk of suicidal thoughts or behavior with AEDs was observed as early as one week after starting drug treatment with AEDs and persisted for the duration of treatment assessed. Because most trials included in the analysis did not extend beyond 24 weeks, the risk of suicidal thoughts or behavior beyond 24 weeks could not be assessed.

The risk of suicidal thoughts or behavior was generally consistent among drugs in the data analyzed. The finding of increased risk with AEDs of varying mechanisms of action and across a range of indications suggests that the risk applies to all AEDs used for any indication. The risk did not vary substantially by age (5-100 years) in the clinical trials analyzed.

Table 3 shows absolute and relative risk by indication for all evaluated AEDs.

Table 3. Risk by Indication for Antiepileptic Drugs in the Pooled Analysis
Indication | Placebo Patients with Events Per 1000 Patients | Drug Patients with Events Per 1000 Patients | Relative Risk: Incidence of Events in Drug Patients/Incidence in Placebo Patients | Risk Difference: Additional Drug Patients with Events Per 1000 Patients
Epilepsy | 1.0 | 3.4 | 3.5 | 2.4
Psychiatric | 5.7 | 8.5 | 1.5 | 2.9
Other | 1.0 | 1.8 | 1.9 | 0.9
Total | 2.4 | 4.3 | 1.8 | 1.9

The relative risk for suicidal thoughts or behavior was higher in clinical trials for epilepsy than in clinical trials for psychiatric or other conditions, but the absolute risk differences were similar for the epilepsy and psychiatric indications.

Anyone considering prescribing LYRICA or any other AED must balance the risk of suicidal thoughts or behavior with the risk of untreated illness. Epilepsy and many other illnesses for which AEDs are prescribed are themselves associated with morbidity and mortality and an increased risk of suicidal thoughts and behavior. Should suicidal thoughts and behavior emerge during treatment, the prescriber needs to consider whether the emergence of these symptoms in any given patient may be related to the illness being treated.

5.4 Increased Risk of Adverse Reactions with Abrupt or Rapid Discontinuation

As with all antiepileptic drugs (AEDs), withdraw LYRICA gradually to minimize the potential of increased seizure frequency in patients with seizure disorders.

Following abrupt or rapid discontinuation of LYRICA, some patients reported symptoms including insomnia, nausea, headache, anxiety, hyperhidrosis, and diarrhea [see Adverse Reactions (6.2), Drug Abuse and Dependence (9.3)]. Suicidal behavior and ideation have also been reported in patients after discontinuation of pregabalin [see Warnings and Precautions (5.3)].

If LYRICA is discontinued, taper the drug gradually over a minimum of 1 week rather than discontinue the drug abruptly.

5.5 Respiratory Depression

There is evidence from case reports, human studies, and animal studies associating LYRICA with serious, life-threatening, or fatal respiratory depression when co-administered with central nervous system (CNS) depressants, including opioids, or in the setting of underlying respiratory impairment. When the decision is made to co-prescribe LYRICA with another CNS depressant, particularly an opioid, or to prescribe LYRICA to patients with underlying respiratory impairment, monitor patients for symptoms of respiratory depression and sedation, and consider initiating LYRICA at a low dose. The management of respiratory depression may include close observation, supportive measures, and reduction or withdrawal of CNS depressants (including LYRICA).

There is more limited evidence from case reports, animal studies, and human studies associating LYRICA with serious respiratory depression, without co-administered CNS depressants or without underlying respiratory impairment.

5.6 Dizziness and Somnolence

LYRICA may cause dizziness and somnolence. Inform patients that LYRICA-related dizziness and somnolence may impair their ability to perform tasks such as driving or operating machinery [see Patient Counseling Information (17)].

In the LYRICA controlled trials in adult patients, dizziness was experienced by 30% of LYRICA-treated patients compared to 8% of placebo-treated patients; somnolence was experienced by 23% of LYRICA-treated patients compared to 8% of placebo-treated patients. Dizziness and somnolence generally began shortly after the initiation of LYRICA therapy and occurred more frequently at higher doses. Dizziness and somnolence were the adverse reactions most frequently leading to withdrawal (4% each) from controlled studies. In LYRICA-treated patients reporting these adverse reactions in short-term, controlled studies, dizziness persisted until the last dose in 30% and somnolence persisted until the last dose in 42% of patients [see Drug Interactions (7)].

In the LYRICA controlled trials in pediatric patients 4 to less than 17 years of age and 1 month to less than 4 years of age for the treatment of partial-onset seizures, somnolence was reported in 21% and 15% of LYRICA-treated patients compared to 14% and 9% of placebo-treated patients, respectively, and occurred more frequently at higher doses. For patients 1 month to less than 4 years of age, somnolence includes related terms lethargy, sluggishness, and hypersomnia.

5.7 Peripheral Edema

LYRICA treatment may cause peripheral edema. In short-term trials of patients without clinically significant heart or peripheral vascular disease, there was no apparent association between peripheral edema and cardiovascular complications such as hypertension or congestive heart failure. Peripheral edema was not associated with laboratory changes suggestive of deterioration in renal or hepatic function.

In controlled clinical trials in adult patients, the incidence of peripheral edema was 6% in the LYRICA group compared with 2% in the placebo group. In controlled clinical trials, 0.5% of LYRICA patients and 0.2% placebo patients withdrew due to peripheral edema.

Higher frequencies of weight gain and peripheral edema were observed in patients taking both LYRICA and a thiazolidinedione antidiabetic agent compared to patients taking either drug alone. The majority of patients using thiazolidinedione antidiabetic agents in the overall safety database were participants in studies of pain associated with diabetic peripheral neuropathy. In this population, peripheral edema was reported in 3% (2/60) of patients who were using thiazolidinedione antidiabetic agents only, 8% (69/859) of patients who were treated with LYRICA only, and 19% (23/120) of patients who were on both LYRICA and thiazolidinedione antidiabetic agents. Similarly, weight gain was reported in 0% (0/60) of patients on thiazolidinediones only; 4% (35/859) of patients on LYRICA only; and 7.5% (9/120) of patients on both drugs.

As the thiazolidinedione class of antidiabetic drugs can cause weight gain and/or fluid retention, possibly exacerbating or leading to heart failure, exercise caution when co-administering LYRICA and these agents.

Because there are limited data on congestive heart failure patients with New York Heart Association (NYHA) Class III or IV cardiac status, exercise caution when using LYRICA in these patients.

5.8 Weight Gain

LYRICA treatment may cause weight gain. In LYRICA controlled clinical trials in adult patients of up to 14 weeks, a gain of 7% or more over baseline weight was observed in 9% of LYRICA‑treated patients and 2% of placebo-treated patients. Few patients treated with LYRICA (0.3%) withdrew from controlled trials due to weight gain. LYRICA associated weight gain was related to dose and duration of exposure but did not appear to be associated with baseline BMI, gender, or age. Weight gain was not limited to patients with edema [see Warnings and Precautions (5.7)].

Although weight gain was not associated with clinically important changes in blood pressure in short-term controlled studies, the long-term cardiovascular effects of LYRICA-associated weight gain are unknown.

Among diabetic patients, LYRICA-treated patients gained an average of 1.6 kg (range: -16 to 16 kg), compared to an average 0.3 kg (range: -10 to 9 kg) weight gain in placebo patients. In a cohort of 333 diabetic patients who received LYRICA for at least 2 years, the average weight gain was 5.2 kg.

While the effects of LYRICA-associated weight gain on glycemic control have not been systematically assessed, in controlled and longer-term open label clinical trials with diabetic patients, LYRICA treatment did not appear to be associated with loss of glycemic control (as measured by HbA1C).

5.9 Tumorigenic Potential

In standard preclinical in vivo lifetime carcinogenicity studies of LYRICA, an unexpectedly high incidence of hemangiosarcoma was identified in two different strains of mice [see Nonclinical Toxicology (13.1)]. The clinical significance of this finding is unknown. Clinical experience during LYRICA’s premarketing development provides no direct means to assess its potential for inducing tumors in humans.

In clinical studies across various patient populations, comprising 6396 patient-years of exposure in patients greater than 12 years of age, new or worsening-preexisting tumors were reported in 57 patients. Without knowledge of the background incidence and recurrence in similar populations not treated with LYRICA, it is impossible to know whether the incidence seen in these cohorts is or is not affected by treatment.

5.10 Ophthalmological Effects

In controlled studies in adult patients, a higher proportion of patients treated with LYRICA reported blurred vision (7%) than did patients treated with placebo (2%), which resolved in a majority of cases with continued dosing. Less than 1% of patients discontinued LYRICA treatment due to vision-related events (primarily blurred vision).

Prospectively planned ophthalmologic testing, including visual acuity testing, formal visual field testing and dilated funduscopic examination, was performed in over 3600 patients. In these patients, visual acuity was reduced in 7% of patients treated with LYRICA, and 5% of placebo‑treated patients. Visual field changes were detected in 13% of LYRICA-treated, and 12% of placebo-treated patients. Funduscopic changes were observed in 2% of LYRICA-treated and 2% of placebo-treated patients.

Although the clinical significance of the ophthalmologic findings is unknown, inform patients to notify their physician if changes in vision occur. If visual disturbance persists, consider further assessment. Consider more frequent assessment for patients who are already routinely monitored for ocular conditions [see Patient Counseling Information (17)].

5.11 Creatine Kinase Elevations

LYRICA treatment was associated with creatine kinase elevations. Mean changes in creatine kinase from baseline to the maximum value were 60 U/L for LYRICA-treated patients and 28 U/L for the placebo patients. In all controlled trials in adult patients across multiple patient populations, 1.5% of patients on LYRICA and 0.7% of placebo patients had a value of creatine kinase at least three times the upper limit of normal. Three LYRICA‑treated subjects had events reported as rhabdomyolysis in premarketing clinical trials. The relationship between these myopathy events and LYRICA is not completely understood because the cases had documented factors that may have caused or contributed to these events. Instruct patients to promptly report unexplained muscle pain, tenderness, or weakness, particularly if these muscle symptoms are accompanied by malaise or fever. Discontinue treatment with LYRICA if myopathy is diagnosed or suspected or if markedly elevated creatine kinase levels occur.

5.12 Decreased Platelet Count

LYRICA treatment was associated with a decrease in platelet count. LYRICA-treated subjects experienced a mean maximal decrease in platelet count of 20 × 10^3/µL, compared to 11 × 10^3/µL in placebo patients. In the overall database of controlled trials in adult patients, 2% of placebo patients and 3% of LYRICA patients experienced a potentially clinically significant decrease in platelets, defined as 20% below baseline value and less than 150 × 10^3/µL. A single LYRICA‑treated subject developed severe thrombocytopenia with a platelet count less than 20 × 10^3/µL. In randomized controlled trials, LYRICA was not associated with an increase in bleeding-related adverse reactions.

5.13 PR Interval Prolongation

LYRICA treatment was associated with PR interval prolongation. In analyses of clinical trial ECG data in adult patients, the mean PR interval increase was 3-6 msec at LYRICA doses greater than or equal to 300 mg/day. This mean change difference was not associated with an increased risk of PR increase greater than or equal to 25% from baseline, an increased percentage of subjects with on-treatment PR greater than 200 msec, or an increased risk of adverse reactions of second or third degree AV block.

Subgroup analyses did not identify an increased risk of PR prolongation in patients with baseline PR prolongation or in patients taking other PR prolonging medications. However, these analyses cannot be considered definitive because of the limited number of patients in these categories.

6 ADVERSE REACTIONS

The following serious adverse reactions are described elsewhere in the labeling:

- Angioedema [see Warnings and Precautions (5.1)]
- Hypersensitivity [see Warnings and Precautions (5.2)]
- Suicidal Behavior and Ideation [see Warnings and Precautions (5.3)]
- Increased Risk of Adverse Reactions with Abrupt or Rapid Discontinuation [see Warnings and Precautions (5.4)]
- Respiratory Depression [see Warnings and Precautions (5.5)]
- Dizziness and Somnolence [see Warnings and Precautions (5.6)]
- Peripheral Edema [see Warnings and Precautions (5.7)]
- Weight Gain [see Warnings and Precautions (5.8)]
- Tumorigenic Potential [see Warnings and Precautions (5.9)]
- Ophthalmological Effects [see Warnings and Precautions (5.10)]
- Creatine Kinase Elevations [see Warnings and Precautions (5.11)]
- Decreased Platelet Count [see Warnings and Precautions (5.12)]
- PR Interval Prolongation [see Warnings and Precautions (5.13)]

6.1 Clinical Trials Experience

Because clinical trials are conducted under widely varying conditions, adverse reaction rates observed in the clinical trials of a drug cannot be directly compared to rates in the clinical trials of another drug and may not reflect the rates observed in practice.

In all controlled and uncontrolled trials across various patient populations during the premarketing development of LYRICA, more than 10,000 patients have received LYRICA. Approximately 5000 patients were treated for 6 months or more, over 3100 patients were treated for 1 year or longer, and over 1400 patients were treated for at least 2 years.

Adverse Reactions Most Commonly Leading to Discontinuation in All Premarketing Controlled Clinical Studies

In premarketing controlled trials of all adult populations combined, 14% of patients treated with LYRICA and 7% of patients treated with placebo discontinued prematurely due to adverse reactions. In the LYRICA treatment group, the adverse reactions most frequently leading to discontinuation were dizziness (4%) and somnolence (4%). In the placebo group, 1% of patients withdrew due to dizziness and less than 1% withdrew due to somnolence. Other adverse reactions that led to discontinuation from controlled trials more frequently in the LYRICA group compared to the placebo group were ataxia, confusion, asthenia, thinking abnormal, blurred vision, incoordination, and peripheral edema (1% each).

Most Common Adverse Reactions in All Controlled Clinical Studies in Adults

In premarketing controlled trials of all adult patient populations combined (including DPN, PHN, and adult patients with partial-onset seizures), dizziness, somnolence, dry mouth, edema, blurred vision, weight gain, and “thinking abnormal” (primarily difficulty with concentration/attention) were more commonly reported by subjects treated with LYRICA than by subjects treated with placebo (greater than or equal to 5% and twice the rate of that seen in placebo).

Controlled Studies with Neuropathic Pain Associated with Diabetic Peripheral Neuropathy

Adverse Reactions Leading to Discontinuation

In clinical trials in adults with neuropathic pain associated with diabetic peripheral neuropathy, 9% of patients treated with LYRICA and 4% of patients treated with placebo discontinued prematurely due to adverse reactions. In the LYRICA treatment group, the most common reasons for discontinuation due to adverse reactions were dizziness (3%) and somnolence (2%). In comparison, less than 1% of placebo patients withdrew due to dizziness and somnolence. Other reasons for discontinuation from the trials, occurring with greater frequency in the LYRICA group than in the placebo group, were asthenia, confusion, and peripheral edema. Each of these events led to withdrawal in approximately 1% of patients.

Most Common Adverse Reactions

Table 4 lists all adverse reactions, regardless of causality, occurring in greater than or equal to 1% of patients with neuropathic pain associated with diabetic neuropathy in the combined LYRICA group for which the incidence was greater in this combined LYRICA group than in the placebo group. A majority of pregabalin-treated patients in clinical studies had adverse reactions with a maximum intensity of “mild” or “moderate”.

Table 4. Adverse Reaction Incidence in Controlled Trials in Neuropathic Pain Associated with Diabetic Peripheral Neuropathy
Body system Preferred term | 75 mg/day [N=77] % | 150 mg/day [N=212] % | 300 mg/day [N=321] % | 600 mg/day [N=369] % | All PGB [PGB: pregabalin] [N=979] % | Placebo [N=459] %
Body as a whole
Asthenia | 4 | 2 | 4 | 7 | 5 | 2
Accidental injury | 5 | 2 | 2 | 6 | 4 | 3
Back pain | 0 | 2 | 1 | 2 | 2 | 0
Chest pain | 4 | 1 | 1 | 2 | 2 | 1
Face edema | 0 | 1 | 1 | 2 | 1 | 0
Digestive system
Dry mouth | 3 | 2 | 5 | 7 | 5 | 1
Constipation | 0 | 2 | 4 | 6 | 4 | 2
Flatulence | 3 | 0 | 2 | 3 | 2 | 1
Metabolic and nutritional disorders
Peripheral edema | 4 | 6 | 9 | 12 | 9 | 2
Weight gain | 0 | 4 | 4 | 6 | 4 | 0
Edema | 0 | 2 | 4 | 2 | 2 | 0
Hypoglycemia | 1 | 3 | 2 | 1 | 2 | 1
Nervous system
Dizziness | 8 | 9 | 23 | 29 | 21 | 5
Somnolence | 4 | 6 | 13 | 16 | 12 | 3
Neuropathy | 9 | 2 | 2 | 5 | 4 | 3
Ataxia | 6 | 1 | 2 | 4 | 3 | 1
Vertigo | 1 | 2 | 2 | 4 | 3 | 1
Confusion | 0 | 1 | 2 | 3 | 2 | 1
Euphoria | 0 | 0 | 3 | 2 | 2 | 0
Incoordination | 1 | 0 | 2 | 2 | 2 | 0
Thinking abnormal [Thinking abnormal primarily consists of events related to difficulty with concentration/attention but also includes events related to cognition and language problems and slowed thinking.] | 1 | 0 | 1 | 3 | 2 | 0
Tremor | 1 | 1 | 1 | 2 | 1 | 0
Abnormal gait | 1 | 0 | 1 | 3 | 1 | 0
Amnesia | 3 | 1 | 0 | 2 | 1 | 0
Nervousness | 0 | 1 | 1 | 1 | 1 | 0
Respiratory system
Dyspnea | 3 | 0 | 2 | 2 | 2 | 1
Special senses
Blurry vision [Investigator term; summary level term is amblyopia] | 3 | 1 | 3 | 6 | 4 | 2
Abnormal vision | 1 | 0 | 1 | 1 | 1 | 0

Controlled Studies in Postherpetic Neuralgia

Adverse Reactions Leading to Discontinuation

In clinical trials in adults with postherpetic neuralgia, 14% of patients treated with LYRICA and 7% of patients treated with placebo discontinued prematurely due to adverse reactions. In the LYRICA treatment group, the most common reasons for discontinuation due to adverse reactions were dizziness (4%) and somnolence (3%). In comparison, less than 1% of placebo patients withdrew due to dizziness and somnolence. Other reasons for discontinuation from the trials, occurring in greater frequency in the LYRICA group than in the placebo group, were confusion (2%), as well as peripheral edema, asthenia, ataxia, and abnormal gait (1% each).

Most Common Adverse Reactions

Table 5 lists all adverse reactions, regardless of causality, occurring in greater than or equal to 1% of patients with neuropathic pain associated with postherpetic neuralgia in the combined LYRICA group for which the incidence was greater in this combined LYRICA group than in the placebo group. In addition, an event is included, even if the incidence in the all LYRICA group is not greater than in the placebo group, if the incidence of the event in the 600 mg/day group is more than twice that in the placebo group. A majority of pregabalin-treated patients in clinical studies had adverse reactions with a maximum intensity of “mild” or “moderate”. Overall, 12.4% of all pregabalin-treated patients and 9.0% of all placebo-treated patients had at least one severe event while 8% of pregabalin-treated patients and 4.3% of placebo-treated patients had at least one severe treatment-related adverse event.

Table 5. Adverse Reaction Incidence in Controlled Trials in Neuropathic Pain Associated with Postherpetic Neuralgia
Body system Preferred term | 75 mg/d [N=84] % | 150 mg/d [N=302] % | 300 mg/d [N=312] % | 600 mg/d [N=154] % | All PGB [PGB: pregabalin] [N=852] % | Placebo [N=398] %
Body as a whole
Infection | 14 | 8 | 6 | 3 | 7 | 4
Headache | 5 | 9 | 5 | 8 | 7 | 5
Pain | 5 | 4 | 5 | 5 | 5 | 4
Accidental injury | 4 | 3 | 3 | 5 | 3 | 2
Flu syndrome | 1 | 2 | 2 | 1 | 2 | 1
Face edema | 0 | 2 | 1 | 3 | 2 | 1
Digestive system
Dry mouth | 7 | 7 | 6 | 15 | 8 | 3
Constipation | 4 | 5 | 5 | 5 | 5 | 2
Flatulence | 2 | 1 | 2 | 3 | 2 | 1
Vomiting | 1 | 1 | 3 | 3 | 2 | 1
Metabolic and nutritional disorders
Peripheral edema | 0 | 8 | 16 | 16 | 12 | 4
Weight gain | 1 | 2 | 5 | 7 | 4 | 0
Edema | 0 | 1 | 2 | 6 | 2 | 1
Musculoskeletal system
Myasthenia | 1 | 1 | 1 | 1 | 1 | 0
Nervous system
Dizziness | 11 | 18 | 31 | 37 | 26 | 9
Somnolence | 8 | 12 | 18 | 25 | 16 | 5
Ataxia | 1 | 2 | 5 | 9 | 5 | 1
Abnormal gait | 0 | 2 | 4 | 8 | 4 | 1
Confusion | 1 | 2 | 3 | 7 | 3 | 0
Thinking abnormal [Thinking abnormal primarily consists of events related to difficulty with concentration/attention but also includes events related to cognition and language problems and slowed thinking.] | 0 | 2 | 1 | 6 | 2 | 2
Incoordination | 2 | 2 | 1 | 3 | 2 | 0
Amnesia | 0 | 1 | 1 | 4 | 2 | 0
Speech disorder | 0 | 0 | 1 | 3 | 1 | 0
Respiratory system
Bronchitis | 0 | 1 | 1 | 3 | 1 | 1
Special senses
Blurry vision [Investigator term; summary level term is amblyopia] | 1 | 5 | 5 | 9 | 5 | 3
Diplopia | 0 | 2 | 2 | 4 | 2 | 0
Abnormal vision | 0 | 1 | 2 | 5 | 2 | 0
Eye Disorder | 0 | 1 | 1 | 2 | 1 | 0
Urogenital System
Urinary Incontinence | 0 | 1 | 1 | 2 | 1 | 0

Controlled Studies of Adjunctive Therapy for Partial-Onset Seizures in Adult Patients

Adverse Reactions Leading to Discontinuation

Approximately 15% of patients receiving LYRICA and 6% of patients receiving placebo in trials of adjunctive therapy for partial‑onset seizures discontinued prematurely due to adverse reactions. In the LYRICA treatment group, the adverse reactions most frequently leading to discontinuation were dizziness (6%), ataxia (4%), and somnolence (3%). In comparison, less than 1% of patients in the placebo group withdrew due to each of these events. Other adverse reactions that led to discontinuation of at least 1% of patients in the LYRICA group and at least twice as frequently compared to the placebo group were asthenia, diplopia, blurred vision, thinking abnormal, nausea, tremor, vertigo, headache, and confusion (which each led to withdrawal in 2% or less of patients).

Most Common Adverse Reactions

Table 6 lists all dose-related adverse reactions occurring in at least 2% of all LYRICA-treated patients. Dose-relatedness was defined as the incidence of the adverse event in the 600 mg/day group was at least 2% greater than the rate in both the placebo and 150 mg/day groups. In these studies, 758 patients received LYRICA and 294 patients received placebo for up to 12 weeks. A majority of pregabalin-treated patients in clinical studies had adverse reactions with a maximum intensity of “mild” or “moderate”.

Table 6. Dose-related Adverse Reaction Incidence in Controlled Trials of Adjunctive Therapy for Partial-Onset Seizures in Adult Patients
Body System; Preferred Term | 150 mg/d; [N=185]; % | 300 mg/d; [N=90]; % | 600 mg/d; [N=395]; % | All PGB [PGB: pregabalin]; [N=670] [Excludes patients who received the 50 mg dose in Study E1.]; % | Placebo; [N=294]; %
Body as a Whole
Accidental Injury | 7 | 11 | 10 | 9 | 5
Pain | 3 | 2 | 5 | 4 | 3
Digestive System
Increased Appetite | 2 | 3 | 6 | 5 | 1
Dry Mouth | 1 | 2 | 6 | 4 | 1
Constipation | 1 | 1 | 7 | 4 | 2
Metabolic and Nutritional Disorders
Weight Gain | 5 | 7 | 16 | 12 | 1
Peripheral Edema | 3 | 3 | 6 | 5 | 2
Nervous System
Dizziness | 18 | 31 | 38 | 32 | 11
Somnolence | 11 | 18 | 28 | 22 | 11
Ataxia | 6 | 10 | 20 | 15 | 4
Tremor | 3 | 7 | 11 | 8 | 4
Thinking Abnormal [Thinking abnormal primarily consists of events related to difficulty with concentration/attention but also includes events related to cognition and language problems and slowed thinking.] | 4 | 8 | 9 | 8 | 2
Amnesia | 3 | 2 | 6 | 5 | 2
Speech Disorder | 1 | 2 | 7 | 5 | 1
Incoordination | 1 | 3 | 6 | 4 | 1
Abnormal Gait | 1 | 3 | 5 | 4 | 0
Twitching | 0 | 4 | 5 | 4 | 1
Confusion | 1 | 2 | 5 | 4 | 2
Myoclonus | 1 | 0 | 4 | 2 | 0
Special Senses
Blurred Vision [Investigator term; summary level term is amblyopia.] | 5 | 8 | 12 | 10 | 4
Diplopia | 5 | 7 | 12 | 9 | 4
Abnormal Vision | 3 | 1 | 5 | 4 | 1

Controlled Study of Adjunctive Therapy for Partial-Onset Seizures in Patients 4 to Less Than 17 Years of Age

Adverse Reactions Leading to Discontinuation

Approximately 2.5% of patients receiving LYRICA and no patients receiving placebo in trials of adjunctive therapy for partial‑onset seizures discontinued prematurely due to adverse reactions. In the LYRICA treatment group, the adverse reactions leading to discontinuation were somnolence (3 patients), worsening of epilepsy (1 patient), and hallucination (1 patient).

Most Common Adverse Reactions

Table 7 lists all dose-related adverse reactions occurring in at least 2% of all LYRICA-treated patients. Dose-relatedness was defined as an incidence of the adverse event in the 10 mg/kg/day group that was at least 2% greater than the rate in both the placebo and 2.5 mg/kg/day groups. In this study, 201 patients received LYRICA and 94 patients received placebo for up to 12 weeks. A majority of pregabalin-treated patients in the clinical study had adverse reactions with a maximum intensity of “mild” or “moderate”.

Table 7. Dose-related Adverse Reaction Incidence in a Controlled Trial in Adjunctive Therapy for Partial‑Onset Seizures in Patients 4 to Less Than 17 Years of Age
Body System; Preferred Term | 2.5 mg/kg/day [2.5 mg/kg/day: Maximum dose 150 mg/day. Includes patients less than 30 kg for whom dose was adjusted to 3.5 mg/kg/day.]; [N=104]; % | 10 mg/kg/day [10 mg/kg/day: Maximum dose 600 mg/day. Includes patients less than 30 kg for whom dose was adjusted to 14 mg/kg/day.]; [N=97]; % | All PGB; [N=201]; % | Placebo; [N=94]; %
Gastrointestinal Disorders
Salivary Hypersecretion | 1 | 4 | 2 | 0
Investigations
Weight Increased | 4 | 13 | 8 | 4
Metabolism and Nutrition Disorders
Increased Appetite | 7 | 10 | 8 | 4
Nervous System Disorders
Somnolence | 17 | 26 | 21 | 14
Abbreviations: N=number of patients; PGB = pregabalin.

Controlled Study of Adjunctive Therapy for Partial-Onset Seizures in Patients 1 Month to Less Than 4 Years of Age

Most Common Adverse Reactions

Table 8 lists all dose-related adverse reactions occurring in at least 2% of all LYRICA-treated patients. Dose-relatedness was defined as an incidence of the adverse event in the 14 mg/kg/day group that was at least 2% greater than the rate in both the placebo and 7 mg/kg/day groups. In this study, 105 patients received LYRICA and 70 patients received placebo for up to 14 days.

Table 8. Dose-related Adverse Reaction Incidence in a Controlled Trial in Adjunctive Therapy for Partial‑Onset Seizures in Patients 1 Month to Less Than 4 Years of Age
Body system; Preferred term | 7 mg/kg/day; [N=71]; % | 14 mg/kg/day; [N=34]; % | All PGB; [N=105]; % | Placebo; [N=70]; %
Nervous system disorders
Somnolence [includes related terms including lethargy, sluggishness, and hypersomnia.] | 13 | 21 | 15 | 9
Infections and infestations
Pneumonia | 1 | 9 | 4 | 0
Viral infection | 3 | 6 | 4 | 3
Abbreviations: N=number of patients; PGB=pregabalin.

Controlled Studies with Fibromyalgia

Adverse Reactions Leading to Discontinuation

In clinical trials of patients with fibromyalgia, 19% of patients treated with pregabalin (150‑600 mg/day) and 10% of patients treated with placebo discontinued prematurely due to adverse reactions. In the pregabalin treatment group, the most common reasons for discontinuation due to adverse reactions were dizziness (6%) and somnolence (3%). In comparison, less than 1% of placebo-treated patients withdrew due to dizziness and somnolence. Other reasons for discontinuation from the trials, occurring with greater frequency in the pregabalin treatment group than in the placebo treatment group, were fatigue, headache, balance disorder, and weight increased. Each of these adverse reactions led to withdrawal in approximately 1% of patients.

Most Common Adverse Reactions

Table 9 lists all adverse reactions, regardless of causality, occurring in greater than or equal to 2% of patients with fibromyalgia in the ‘all pregabalin’ treatment group for which the incidence was greater than in the placebo treatment group. A majority of pregabalin-treated patients in clinical studies experienced adverse reactions with a maximum intensity of “mild” or “moderate”.

Table 9. Adverse Reaction Incidence in Controlled Trials in Fibromyalgia
System Organ Class; Preferred term | 150 mg/d [N=132] % | 300 mg/d [N=502] % | 450 mg/d [N=505] % | 600 mg/d [N=378] % | All PGB [PGB: pregabalin] [N=1517] % | Placebo [N=505] %
Ear and Labyrinth Disorders
Vertigo | 2 | 2 | 2 | 1 | 2 | 0
Eye Disorders
Vision blurred | 8 | 7 | 7 | 12 | 8 | 1
Gastrointestinal Disorders
Dry mouth | 7 | 6 | 9 | 9 | 8 | 2
Constipation | 4 | 4 | 7 | 10 | 7 | 2
Vomiting | 2 | 3 | 3 | 2 | 3 | 2
Flatulence | 1 | 1 | 2 | 2 | 2 | 1
Abdominal distension | 2 | 2 | 2 | 2 | 2 | 1
General Disorders and Administrative Site Conditions
Fatigue | 5 | 7 | 6 | 8 | 7 | 4
Edema peripheral | 5 | 5 | 6 | 9 | 6 | 2
Chest pain | 2 | 1 | 1 | 2 | 2 | 1
Feeling abnormal | 1 | 3 | 2 | 2 | 2 | 0
Edema | 1 | 2 | 1 | 2 | 2 | 1
Feeling drunk | 1 | 2 | 1 | 2 | 2 | 0
Infections and Infestations
Sinusitis | 4 | 5 | 7 | 5 | 5 | 4
Investigations
Weight increased | 8 | 10 | 10 | 14 | 11 | 2
Metabolism and Nutrition Disorders
Increased appetite | 4 | 3 | 5 | 7 | 5 | 1
Fluid retention | 2 | 3 | 3 | 2 | 2 | 1
Musculoskeletal and Connective Tissue Disorders
Arthralgia | 4 | 3 | 3 | 6 | 4 | 2
Muscle spasms | 2 | 4 | 4 | 4 | 4 | 2
Back pain | 2 | 3 | 4 | 3 | 3 | 3
Nervous System Disorders
Dizziness | 23 | 31 | 43 | 45 | 38 | 9
Somnolence | 13 | 18 | 22 | 22 | 20 | 4
Headache | 11 | 12 | 14 | 10 | 12 | 12
Disturbance in attention | 4 | 4 | 6 | 6 | 5 | 1
Balance disorder | 2 | 3 | 6 | 9 | 5 | 0
Memory impairment | 1 | 3 | 4 | 4 | 3 | 0
Coordination abnormal | 2 | 1 | 2 | 2 | 2 | 1
Hypoesthesia | 2 | 2 | 3 | 2 | 2 | 1
Lethargy | 2 | 2 | 1 | 2 | 2 | 0
Tremor | 0 | 1 | 3 | 2 | 2 | 0
Psychiatric Disorders
Euphoric Mood | 2 | 5 | 6 | 7 | 6 | 1
Confusional state | 0 | 2 | 3 | 4 | 3 | 0
Anxiety | 2 | 2 | 2 | 2 | 2 | 1
Disorientation | 1 | 0 | 2 | 1 | 2 | 0
Depression | 2 | 2 | 2 | 2 | 2 | 2
Respiratory, Thoracic and Mediastinal Disorders
Pharyngolaryngeal pain | 2 | 1 | 3 | 3 | 2 | 2

Controlled Studies in Neuropathic Pain Associated with Spinal Cord Injury

Adverse Reactions Leading to Discontinuation

In clinical trials of adults with neuropathic pain associated with spinal cord injury, 13% of patients treated with pregabalin and 10% of patients treated with placebo discontinued prematurely due to adverse reactions. In the pregabalin treatment group, the most common reasons for discontinuation due to adverse reactions were somnolence (3%) and edema (2%). In comparison, none of the placebo-treated patients withdrew due to somnolence and edema. Other reasons for discontinuation from the trials, occurring with greater frequency in the pregabalin treatment group than in the placebo treatment group, were fatigue and balance disorder. Each of these adverse reactions led to withdrawal in less than 2% of patients.

Most Common Adverse Reactions

Table 10 lists all adverse reactions, regardless of causality, occurring in greater than or equal to 2% of patients for which the incidence was greater than in the placebo treatment group with neuropathic pain associated with spinal cord injury in the controlled trials. A majority of pregabalin-treated patients in clinical studies experienced adverse reactions with a maximum intensity of “mild” or “moderate”.

Table 10. Adverse Reaction Incidence in Controlled Trials in Neuropathic Pain Associated with Spinal Cord Injury
System Organ Class; Preferred term | PGB [PGB: Pregabalin] (N=182) | Placebo (N=174)
System Organ Class; Preferred term | % | %
Ear and labyrinth disorders
Vertigo | 2.7 | 1.1
Eye disorders
Vision blurred | 6.6 | 1.1
Gastrointestinal disorders
Dry mouth | 11.0 | 2.9
Constipation | 8.2 | 5.7
Nausea | 4.9 | 4.0
Vomiting | 2.7 | 1.1
General disorders and administration site conditions
Fatigue | 11.0 | 4.0
Edema peripheral | 10.4 | 5.2
Edema | 8.2 | 1.1
Pain | 3.3 | 1.1
Infections and infestations
Nasopharyngitis | 8.2 | 4.6
Investigations
Weight increased | 3.3 | 1.1
Blood creatine phosphokinase increased | 2.7 | 0
Musculoskeletal and connective tissue disorders
Muscular weakness | 4.9 | 1.7
Pain in extremity | 3.3 | 2.3
Neck pain | 2.7 | 1.1
Back pain | 2.2 | 1.7
Joint swelling | 2.2 | 0
Nervous system disorders
Somnolence | 35.7 | 11.5
Dizziness | 20.9 | 6.9
Disturbance in attention | 3.8 | 0
Memory impairment | 3.3 | 1.1
Paresthesia | 2.2 | 0.6
Psychiatric disorders
Insomnia | 3.8 | 2.9
Euphoric mood | 2.2 | 0.6
Renal and urinary disorders
Urinary incontinence | 2.7 | 1.1
Skin and subcutaneous tissue disorders
Decubitus ulcer | 2.7 | 1.1
Vascular disorders
Hypertension | 2.2 | 1.1
Hypotension | 2.2 | 0

Other Adverse Reactions Observed During the Clinical Studies of LYRICA

Following is a list of treatment-emergent adverse reactions reported by patients treated with LYRICA during all clinical trials. The listing does not include those events already listed in the previous tables or elsewhere in labeling, those events for which a drug cause was remote, those events which were so general as to be uninformative, and those events reported only once which did not have a substantial probability of being acutely life-threatening.

Events are categorized by body system and listed in order of decreasing frequency according to the following definitions: frequent adverse reactions are those occurring on one or more occasions in at least 1/100 patients; infrequent adverse reactions are those occurring in 1/100 to 1/1000 patients; rare reactions are those occurring in fewer than 1/1000 patients. Events of major clinical importance are described in the Warnings and Precautions section (5).

Body as a Whole – Frequent: Abdominal pain, Allergic reaction, Fever, Infrequent: Abscess, Cellulitis, Chills, Malaise, Neck rigidity, Overdose, Pelvic pain, Photosensitivity reaction, Rare: Anaphylactoid reaction, Ascites, Granuloma, Hangover effect, Intentional Injury, Retroperitoneal Fibrosis, Shock

Cardiovascular System – Infrequent: Deep thrombophlebitis, Heart failure, Hypotension, Postural hypotension, Retinal vascular disorder, Syncope; Rare: ST Depressed, Ventricular Fibrillation

Digestive System – Frequent: Gastroenteritis, Increased appetite; Infrequent: Cholecystitis, Cholelithiasis, Colitis, Dysphagia, Esophagitis, Gastritis, Gastrointestinal hemorrhage, Melena, Mouth ulceration, Pancreatitis, Rectal hemorrhage, Tongue edema; Rare: Aphthous stomatitis, Esophageal Ulcer, Periodontal abscess

Hemic and Lymphatic System – Frequent: Ecchymosis; Infrequent: Anemia, Eosinophilia, Hypochromic anemia, Leukocytosis, Leukopenia, Lymphadenopathy, Thrombocytopenia; Rare: Myelofibrosis, Polycythemia, Prothrombin decreased, Purpura, Thrombocythemia, Alanine aminotransferase increased, Aspartate aminotransferase increased

Metabolic and Nutritional Disorders – Rare: Glucose Tolerance Decreased, Urate Crystalluria

Musculoskeletal System – Frequent: Arthralgia, Leg cramps, Myalgia, Myasthenia; Infrequent: Arthrosis; Rare: Chondrodystrophy, Generalized Spasm

Nervous System – Frequent: Anxiety, Depersonalization, Hypertonia, Hypoesthesia, Libido decreased, Nystagmus, Paresthesia, Sedation, Stupor, Twitching; Infrequent: Abnormal dreams, Agitation, Apathy, Aphasia, Circumoral paresthesia, Dysarthria, Hallucinations, Hostility, Hyperalgesia, Hyperesthesia, Hyperkinesia, Hypokinesia, Hypotonia, Libido increased, Myoclonus, Neuralgia; Rare: Addiction, Cerebellar syndrome, Cogwheel rigidity, Coma, Delirium, Delusions, Dysautonomia, Dyskinesia, Dystonia, Encephalopathy, Extrapyramidal syndrome, Guillain-Barré syndrome, Hypalgesia, Intracranial hypertension, Manic reaction, Paranoid reaction, Peripheral neuritis, Personality disorder, Psychotic depression, Schizophrenic reaction, Sleep disorder, Torticollis, Trismus

Respiratory System – Rare: Apnea, Atelectasis, Bronchiolitis, Hiccup, Laryngismus, Lung edema, Lung fibrosis, Yawn

Skin and Appendages – Frequent: Pruritus, Infrequent: Alopecia, Dry skin, Eczema, Hirsutism, Skin ulcer, Urticaria, Vesiculobullous rash; Rare: Angioedema, Exfoliative dermatitis, Lichenoid dermatitis, Melanosis, Nail Disorder, Petechial rash, Purpuric rash, Pustular rash, Skin atrophy, Skin necrosis, Skin nodule, Stevens-Johnson syndrome, Subcutaneous nodule

Special senses – Frequent: Conjunctivitis, Diplopia, Otitis media, Tinnitus; Infrequent: Abnormality of accommodation, Blepharitis, Dry eyes, Eye hemorrhage, Hyperacusis, Photophobia, Retinal edema, Taste loss, Taste perversion; Rare: Anisocoria, Blindness, Corneal ulcer, Exophthalmos, Extraocular palsy, Iritis, Keratitis, Keratoconjunctivitis, Miosis, Mydriasis, Night blindness, Ophthalmoplegia, Optic atrophy, Papilledema, Parosmia, Ptosis, Uveitis

Urogenital System – Frequent: Anorgasmia, Impotence, Urinary frequency, Urinary incontinence; Infrequent: Abnormal ejaculation, Albuminuria, Amenorrhea, Dysmenorrhea, Dysuria, Hematuria, Kidney calculus, Leukorrhea, Menorrhagia, Metrorrhagia, Nephritis, Oliguria, Urinary retention, Urine abnormality; Rare: Acute kidney failure, Balanitis, Bladder Neoplasm, Cervicitis, Dyspareunia, Epididymitis, Female lactation, Glomerulitis, Ovarian disorder, Pyelonephritis

Comparison of Gender and Race

The overall adverse event profile of pregabalin was similar between women and men. There are insufficient data to support a statement regarding the distribution of adverse experience reports by race.

6.2 Postmarketing Experience

The following adverse reactions have been identified during postapproval use of LYRICA. Because these reactions are reported voluntarily from a population of uncertain size, it is not always possible to reliably estimate their frequency or establish a causal relationship to drug exposure.

Nervous System Disorders – Headache

Gastrointestinal Disorders – Nausea, Diarrhea

Reproductive System and Breast Disorders – Gynecomastia, Breast Enlargement

Skin and subcutaneous tissue disorders – Bullous pemphigoid

There are postmarketing reports of life-threatening or fatal respiratory depression in patients taking LYRICA with opioids or other CNS depressants, or in the setting of underlying respiratory impairment.

In addition, there are postmarketing reports of events related to reduced lower gastrointestinal tract function (e.g., intestinal obstruction, paralytic ileus, constipation) when LYRICA was co-administered with medications that have the potential to produce constipation, such as opioid analgesics.

There are postmarketing reports of withdrawal symptoms after discontinuation of pregabalin. Reported adverse reactions include, but are not limited to, seizures, depression, suicidal ideation and behavior, agitation, confusion, disorientation, psychotic symptoms, anxiety, insomnia, nausea, pain, sweating, tremor, headache, dizziness, malaise, and diarrhea.

7 DRUG INTERACTIONS

Since LYRICA is predominantly excreted unchanged in the urine, undergoes negligible metabolism in humans (less than 2% of a dose recovered in urine as metabolites), and does not bind to plasma proteins, its pharmacokinetics are unlikely to be affected by other agents through metabolic interactions or protein binding displacement. In vitro and in vivo studies showed that LYRICA is unlikely to be involved in significant pharmacokinetic drug interactions. Specifically, there are no pharmacokinetic interactions between pregabalin and the following antiepileptic drugs: carbamazepine, valproic acid, lamotrigine, phenytoin, phenobarbital, and topiramate. Important pharmacokinetic interactions would also not be expected to occur between LYRICA and commonly used antiepileptic drugs [see Clinical Pharmacology (12)].

Pharmacodynamics

Multiple oral doses of LYRICA were co-administered with oxycodone, lorazepam, or ethanol. Although no pharmacokinetic interactions were seen, additive effects on cognitive and gross motor functioning were seen when LYRICA was co-administered with these drugs. No clinically important effects on respiration were seen.

8 USE IN SPECIFIC POPULATIONS

8.1 Pregnancy

Pregnancy Exposure Registry

There is a pregnancy exposure registry that monitors pregnancy outcomes in women exposed to LYRICA during pregnancy. To provide information regarding the effects of in utero exposure to LYRICA, physicians are advised to recommend that pregnant patients taking LYRICA enroll in the North American Antiepileptic Drug (NAAED) Pregnancy Registry. This can be done by calling the toll free number 1-888-233-2334, and must be done by patients themselves. Information on the registry can also be found at the website http://www.aedpregnancyregistry.org/.

Risk Summary

Observational studies on the use of Lyrica during pregnancy suggest a possible small increase in the rate of overall major birth defects, but there was no consistent or specific pattern of major birth defects identified (see Data). Available postmarketing data on miscarriage and other maternal, fetal, and long term developmental adverse effects were insufficient to identify risk associated with pregabalin.

Postmarketing data suggest that extended gabapentinoid use with opioids close to delivery may increase the risk of neonatal withdrawal versus opioids alone (see Clinical Considerations). There are no comparative epidemiologic studies evaluating this association. Therefore, it is not known whether exposure to pregabalin alone late in pregnancy may cause withdrawal signs and symptoms.

In animal reproduction studies, increased incidences of fetal structural abnormalities and other manifestations of developmental toxicity, including skeletal malformations, retarded ossification, and decreased fetal body weight were observed in the offspring of rats and rabbits given pregabalin orally during organogenesis, at doses that produced plasma pregabalin exposures (AUC) greater than or equal to 16 times human exposure at the maximum recommended dose (MRD) of 600 mg/day (see Data). In an animal development study, lethality, growth retardation, and nervous and reproductive system functional impairment were observed in the offspring of rats given pregabalin during gestation and lactation. The no-effect dose for developmental toxicity was approximately twice the human exposure at MRD.

The estimated background risk of major birth defects and miscarriage for the indicated populations are unknown. All pregnancies have a background risk of birth defect, loss, or other adverse outcomes. In the U.S. general population, the estimated background risk of major birth defects and miscarriage in clinically recognized pregnancies is 2 to 4% and 15 to 20%, respectively.

Clinical Considerations

Fetal/Neonatal Adverse Reactions

Neonatal withdrawal syndrome has been reported in newborns exposed to gabapentinoids in utero for an extended period of time when also exposed to opioids close to delivery. Neonatal withdrawal signs and symptoms reported have included tachypnea, vomiting, diarrhea, hypertonia, irritability, sneezing, poor feeding, hyperactivity, abnormal sleep pattern, and tremor. Reported signs and symptoms that may also be related to withdrawal include tongue thrusting, wandering eye movements while awake, back arching, and continuous extremity movements. Observe neonates exposed to LYRICA and opioids for signs and symptoms of neonatal withdrawal and manage accordingly.

Data

Human Data

One database study, which included over 2,700 pregnancies exposed to pregabalin (monotherapy) during the first trimester compared to 3,063,251 pregnancies unexposed to antiepileptics demonstrated prevalence ratios for major malformations overall of 1.14 (CI 95% 0.96-1.35) for pregabalin, 1.29 (CI 95% 1.01-1.65) for lamotrigine, 1.39 (CI 95% 1.07-1.82) for duloxetine, and 1.24 (CI 95% 1.00-1.54) for exposure to either lamotrigine or duloxetine. Important study limitations include uncertainty of whether women who filled a prescription took the medication and inability to adequately control for the underlying disease and other potential confounders.

A published study included results from two separate databases. One database, which included 353 pregnancies exposed to pregabalin (monotherapy) during the first trimester compared to 368,489 pregnancies unexposed to antiepileptics, showed no increase in risk of major birth defects; adjusted relative risk 0.87 (CI 95% 0.53-1.42). The second database, which included 118 pregnancies exposed to pregabalin (monotherapy) during the first trimester compared to 380,347 pregnancies unexposed to antiepileptics, suggested a small increase in risk of major birth defects; adjusted relative risk 1.26 (CI 95% 0.64-2.49). The risk estimates crossed the null, and the study had limitations similar to the prior study.

Other published epidemiologic studies reported inconsistent findings. No specific pattern of birth defects was identified across studies. All of the studies had limitations due to their retrospective design.

Animal Data

When pregnant rats were given pregabalin (500, 1250, or 2500 mg/kg) orally throughout the period of organogenesis, incidences of specific skull alterations attributed to abnormally advanced ossification (premature fusion of the jugal and nasal sutures) were increased at greater than or equal to 1250 mg/kg, and incidences of skeletal variations and retarded ossification were increased at all doses. Fetal body weights were decreased at the highest dose. The low dose in this study was associated with a plasma exposure (AUC) approximately 17 times human exposure at the MRD of 600 mg/day. A no-effect dose for rat embryo-fetal developmental toxicity was not established.

When pregnant rabbits were given LYRICA (250, 500, or 1250 mg/kg) orally throughout the period of organogenesis, decreased fetal body weight and increased incidences of skeletal malformations, visceral variations, and retarded ossification were observed at the highest dose. The no-effect dose for developmental toxicity in rabbits (500 mg/kg) was associated with a plasma exposure approximately 16 times human exposure at the MRD.

In a study in which female rats were dosed with LYRICA (50, 100, 250, 1250, or 2500 mg/kg) throughout gestation and lactation, offspring growth was reduced at greater than or equal to 100 mg/kg and offspring survival was decreased at greater than or equal to 250 mg/kg. The effect on offspring survival was pronounced at doses greater than or equal to 1250 mg/kg, with 100% mortality in high-dose litters. When offspring were tested as adults, neurobehavioral abnormalities (decreased auditory startle responding) were observed at greater than or equal to 250 mg/kg and reproductive impairment (decreased fertility and litter size) was seen at 1250 mg/kg. The no-effect dose for pre- and postnatal developmental toxicity in rats (50 mg/kg) produced a plasma exposure approximately 2 times human exposure at the MRD.

In the prenatal-postnatal study in rats, pregabalin prolonged gestation and induced dystocia at exposures greater than or equal to 50 times the mean human exposure (AUC (0–24) of 123 µg∙hr/mL) at the MRD.

8.2 Lactation

Risk Summary

Small amounts of pregabalin have been detected in the milk of lactating women. A pharmacokinetic study in lactating women detected pregabalin in breast milk at average steady state concentrations approximately 76% of those in maternal plasma. The estimated average daily infant dose of pregabalin from breast milk (assuming mean milk consumption of 150 mL/kg/day) was 0.31 mg/kg/day, which on a mg/kg basis would be approximately 7% of the maternal dose (see Data). The study did not evaluate the effects of LYRICA on milk production or the effects of LYRICA on the breastfed infant.

Based on animal studies, there is a potential risk of tumorigenicity with pregabalin exposure via breast milk to the breastfed infant [see Nonclinical Toxicology (13.1)]. Available clinical study data in patients greater than 12 years of age do not provide a clear conclusion about the potential risk of tumorigenicity with pregabalin [see Warnings and Precautions (5.9)]. Because of the potential risk of tumorigenicity, breastfeeding is not recommended during treatment with LYRICA.

Data

A pharmacokinetic study in ten lactating women, who were at least 12 weeks postpartum, evaluated the concentrations of pregabalin in plasma and breast milk. LYRICA 150 mg oral capsule was given every 12 hours (300 mg daily dose) for a total of four doses. Pregabalin was detected in breast milk at average steady‑state concentrations approximately 76% of those in maternal plasma. The estimated average daily infant dose of pregabalin from breast milk (assuming mean milk consumption of 150 mL/kg/day) was 0.31 mg/kg/day, which on a mg/kg basis would be approximately 7% of the maternal dose. The study did not evaluate the effects of LYRICA on milk production. Infants did not receive breast milk obtained during the dosing period, therefore, the effects of LYRICA on the breast fed infant were not evaluated.

8.3 Females and Males of Reproductive Potential

Infertility

Males

Effects on Spermatogenesis

In a randomized, double-blind, placebo-controlled non-inferiority study to assess the effect of pregabalin on sperm characteristics, healthy male subjects received pregabalin at a daily dose up to 600 mg (n=111) or placebo (n=109) for 13 weeks (one complete sperm cycle) followed by a 13-week washout period (off-drug). A total of 65 subjects in the pregabalin group (59%) and 62 subjects in the placebo group (57%) were included in the per protocol (PP) population. These subjects took study drug for at least 8 weeks, had appropriate timing of semen collections and did not have any significant protocol violations. Among these subjects, approximately 9% of the pregabalin group (6/65) vs. 3% in the placebo group (2/62) had greater than or equal to 50% reduction in mean sperm concentrations from baseline at Week 26 (the primary endpoint). The difference between pregabalin and placebo was within the pre-specified non-inferiority margin of 20%. There were no adverse effects of pregabalin on sperm morphology, sperm motility, serum FSH or serum testosterone levels as compared to placebo. In subjects in the PP population with greater than or equal to 50% reduction in sperm concentration from baseline, sperm concentrations were no longer reduced by greater than or equal to 50% in any affected subject after an additional 3 months off-drug. In one subject, however, subsequent semen analyses demonstrated reductions from baseline of greater than or equal to 50% at 9 and 12 months off‑drug. The clinical relevance of these data is unknown.

In the animal fertility study with pregabalin in male rats, adverse reproductive and developmental effects were observed [see Nonclinical Toxicology (13.1)].

8.4 Pediatric Use

Neuropathic Pain Associated with Diabetic Peripheral Neuropathy, Postherpetic Neuralgia, and Neuropathic Pain Associated with Spinal Cord Injury

Safety and effectiveness in pediatric patients have not been established.

Fibromyalgia

Safety and effectiveness in pediatric patients have not been established.

A 15-week, placebo-controlled trial was conducted with 107 pediatric patients with fibromyalgia, ages 12 through 17 years, at LYRICA total daily doses of 75‑450 mg per day. The primary efficacy endpoint of change from baseline to Week 15 in mean pain intensity (derived from an 11‑point numeric rating scale) showed numerically greater improvement for the pregabalin‑treated patients compared to placebo‑treated patients, but did not reach statistical significance. The most frequently observed adverse reactions in the clinical trial included dizziness, nausea, headache, weight increased, and fatigue. The overall safety profile in adolescents was similar to that observed in adults with fibromyalgia.

Adjunctive Therapy for Partial-Onset Seizures

Safety and effectiveness in pediatric patients below the age of 1 month have not been established.

4 to Less Than 17 Years of Age with Partial-Onset Seizures

The safety and effectiveness of LYRICA as adjunctive treatment for partial‑onset seizures in pediatric patients 4 to less than 17 years of age have been established in a 12-week, double-blind, placebo-controlled study (n=295) [see Clinical Studies (14.3)]. Patients treated with LYRICA 10 mg/kg/day had, on average, a 21.0% greater reduction in partial‑onset seizures than patients treated with placebo (p=0.0185). Patients treated with LYRICA 2.5 mg/kg/day had, on average, a 10.5% greater reduction in partial‑onset seizures than patients treated with placebo, but the difference was not statistically significant (p=0.2577).

Responder rates (50% or greater reduction in partial‑onset seizure frequency) were a key secondary efficacy parameter and showed numerical improvement with LYRICA compared with placebo: the responder rates were 40.6%, 29.1%, and 22.6%, for LYRICA 10 mg/kg/day, LYRICA 2.5 mg/kg/day, and placebo, respectively.

The most common adverse reactions (≥5%) with LYRICA in this study were somnolence, weight increased, and increased appetite [see Adverse Reactions (6.1)].

The use of LYRICA 2.5 mg/kg/day in pediatric patients is further supported by evidence from adequate and well‑controlled studies in adults with partial-onset seizures and pharmacokinetic data from adult and pediatric patients [see Clinical Pharmacology (12.3)].

1 Month to Less than 4 Years of Age with Partial-Onset Seizures

The safety and effectiveness of LYRICA as adjunctive treatment for partial‑onset seizures in pediatric patients 1 month to less than 4 years of age have been established in a 14‑day double‑blind, placebo-controlled study (N=175) [see Clinical Studies (14.3)]. The youngest subject evaluated was 3 months of age; use in patients 1 month to less than 3 months of age is supported by additional pharmacokinetic analyses. Patients treated with LYRICA 14 mg/kg/day had, on average, 43.9% greater reduction in partial‑onset seizures than patients treated with placebo (p=0.0223). In addition, pediatric patients treated with LYRICA 14 mg/kg/day showed numerical improvement in responder rates (≥50% reduction in partial‑onset seizure frequency) compared with placebo (53.6% versus 41.5%). Patients treated with LYRICA 7 mg/kg/day did not show improvement relative to placebo for either endpoint.

The most common dose‑related adverse reactions (>5%) with LYRICA in this study were somnolence, pneumonia, and viral infection [see Adverse Reactions (6.1)].

Juvenile Animal Data

In studies in which pregabalin (50 to 500 mg/kg) was orally administered to young rats from early in the postnatal period (Postnatal Day 7) through sexual maturity, neurobehavioral abnormalities (deficits in learning and memory, altered locomotor activity, decreased auditory startle responding and habituation) and reproductive impairment (delayed sexual maturation and decreased fertility in males and females) were observed at doses greater than or equal to 50 mg/kg. The neurobehavioral changes of acoustic startle persisted at greater than or equal to 250 mg/kg and locomotor activity and water maze performance at greater than or equal to 500 mg/kg in animals tested after cessation of dosing and, thus, were considered to represent long-term effects. The low effect dose for developmental neurotoxicity and reproductive impairment in juvenile rats (50 mg/kg) was associated with a plasma pregabalin exposure (AUC) approximately equal to human exposure at the maximum recommended dose of 600 mg/day. A no-effect dose was not established.

8.5 Geriatric Use

In controlled clinical studies of LYRICA in neuropathic pain associated with diabetic peripheral neuropathy, 246 patients were 65 to 74 years of age, and 73 patients were 75 years of age or older.

In controlled clinical studies of LYRICA in neuropathic pain associated with postherpetic neuralgia, 282 patients were 65 to 74 years of age, and 379 patients were 75 years of age or older.

In controlled clinical studies of LYRICA in epilepsy, there were only 10 patients 65 to 74 years of age, and 2 patients who were 75 years of age or older.

No overall differences in safety and efficacy were observed between these patients and younger patients.

In controlled clinical studies of LYRICA in fibromyalgia, 106 patients were 65 years of age or older. Although the adverse reaction profile was similar between the two age groups, the following neurological adverse reactions were more frequent in patients 65 years of age or older: dizziness, vision blurred, balance disorder, tremor, confusional state, coordination abnormal, and lethargy.

LYRICA is known to be substantially excreted by the kidney, and the risk of toxic reactions to LYRICA may be greater in patients with impaired renal function. Because LYRICA is eliminated primarily by renal excretion, adjust the dose for elderly patients with renal impairment [see Dosage and Administration (2.7)].

8.6 Renal Impairment

LYRICA is eliminated primarily by renal excretion and dose adjustment is recommended for adult patients with renal impairment [see Dosage and Administration (2.7) and Clinical Pharmacology (12.3)]. The use of LYRICA in pediatric patients with compromised renal function has not been studied.

9 DRUG ABUSE AND DEPENDENCE

9.1 Controlled Substance

LYRICA is a Schedule V controlled substance.

LYRICA is not known to be active at receptor sites associated with drugs of abuse. As with any CNS active drug, carefully evaluate patients for history of drug abuse and observe them for signs of LYRICA misuse or abuse (e.g., development of tolerance, dose escalation, drug-seeking behavior).

9.2 Abuse

In a study of recreational users (N=15) of sedative/hypnotic drugs, including alcohol, LYRICA (450 mg, single dose) received subjective ratings of "good drug effect," "high" and "liking" to a degree that was similar to diazepam (30 mg, single dose). In controlled clinical studies in over 5500 patients, 4 % of LYRICA-treated patients and 1 % of placebo-treated patients overall reported euphoria as an adverse reaction, though in some patient populations studied, this reporting rate was higher and ranged from 1 to 12%.

9.3 Dependence

In clinical studies, following abrupt or rapid discontinuation of LYRICA, some patients reported symptoms including insomnia, nausea, headache or diarrhea [see Warnings and Precautions (5.4)], consistent with physical dependence. In the postmarketing setting, in addition to these reported symptoms, other reported adverse reactions include, but are not limited to, seizures, depression, suicidal ideation and behavior, agitation, confusion, disorientation, psychotic symptoms, pain, sweating, tremor, dizziness, and malaise.

10 OVERDOSAGE

Signs, Symptoms and Laboratory Findings of Acute Overdosage in Humans

In the postmarketing experience, the most commonly reported adverse events observed with pregabalin when taken in overdose include reduced consciousness, depression/anxiety, confusional state, agitation, and restlessness. Seizures and heart block have also been reported. Deaths have been reported in the setting of lone LYRICA overdose and in combination with other CNS depressants.

Treatment or Management of Overdose

There is no specific antidote for overdose with LYRICA. If indicated, elimination of unabsorbed drug may be attempted by emesis or gastric lavage; observe usual precautions to maintain the airway. General supportive care of the patient is indicated including monitoring of vital signs and observation of the clinical status of the patient. Contact a Certified Poison Control Center for up‑to-date information on the management of overdose with LYRICA.

LYRICA can be removed by hemodialysis. Standard hemodialysis procedures result in significant clearance of pregabalin (approximately 50% in 4 hours).

11 DESCRIPTION

Pregabalin is described chemically as (S)-3-(aminomethyl)-5-methylhexanoic acid. The molecular formula is C8H17NO2 and the molecular weight is 159.23. The chemical structure of pregabalin is:

Pregabalin is a white to off-white, crystalline solid with a pKa1 of 4.2 and a pKa2 of 10.6. It is freely soluble in water and both basic and acidic aqueous solutions. The log of the partition coefficient (n-octanol/0.05M phosphate buffer) at pH 7.4 is -1.35.

LYRICA (pregabalin) Capsules are administered orally and are supplied as imprinted hard-shell capsules containing 25, 50, 75, 100, 150, 200, 225, and 300 mg of pregabalin, along with cornstarch, lactose monohydrate, and talc as inactive ingredients. The capsule shells contain gelatin and titanium dioxide. In addition, the orange capsule shells contain red iron oxide and the white capsule shells contain colloidal silicon dioxide and sodium lauryl sulfate. Colloidal silicon dioxide is a manufacturing aid that may or may not be present in the capsule shells. The imprinting ink contains black iron oxide, potassium hydroxide, propylene glycol, and shellac.

LYRICA (pregabalin) oral solution, 20 mg/mL, is administered orally and is supplied as a clear, colorless solution contained in a 16 fluid ounce white HDPE bottle with a polyethylene-lined closure. The oral solution contains 20 mg/mL of pregabalin, along with artificial strawberry #11545, dibasic sodium phosphate anhydrous, methylparaben, monobasic sodium phosphate anhydrous, propylparaben, purified water, and sucralose as inactive ingredients.

12 CLINICAL PHARMACOLOGY

12.1 Mechanism of Action

LYRICA (pregabalin) binds with high affinity to the alpha2-delta site (an auxiliary subunit of voltage-gated calcium channels) in central nervous system tissues. Although the mechanism of action of pregabalin has not been fully elucidated, results with genetically modified mice and with compounds structurally related to pregabalin (such as gabapentin) suggest that binding to the alpha2-delta subunit may be involved in pregabalin’s anti-nociceptive and antiseizure effects in animals. In animal models of nerve damage, pregabalin has been shown to reduce calcium-dependent release of pro-nociceptive neurotransmitters in the spinal cord, possibly by disrupting alpha2-delta containing-calcium channel trafficking and/or reducing calcium currents. Evidence from other animal models of nerve damage and persistent pain suggest the anti-nociceptive activities of pregabalin may also be mediated through interactions with descending noradrenergic and serotonergic pathways originating from the brainstem that modulate pain transmission in the spinal cord.

While pregabalin is a structural derivative of the inhibitory neurotransmitter gamma-aminobutyric acid (GABA), it does not bind directly to GABAA, GABAB, or benzodiazepine receptors, does not augment GABAA responses in cultured neurons, does not alter rat brain GABA concentration or have acute effects on GABA uptake or degradation. However, in cultured neurons prolonged application of pregabalin increases the density of GABA transporter protein and increases the rate of functional GABA transport. Pregabalin does not block sodium channels, is not active at opiate receptors, and does not alter cyclooxygenase enzyme activity. It is inactive at serotonin and dopamine receptors and does not inhibit dopamine, serotonin, or noradrenaline reuptake.

12.3 Pharmacokinetics

Pregabalin is well absorbed after oral administration, is eliminated largely by renal excretion, and has an elimination half-life of about 6 hours.

Absorption and Distribution

Following oral administration of LYRICA capsules under fasting conditions, peak plasma concentrations occur within 1.5 hours. Pregabalin oral bioavailability is greater than or equal to 90% and is independent of dose. Following single- (25 to 300 mg) and multiple-dose (75 to 900 mg/day) administration, maximum plasma concentrations (Cmax) and area under the plasma concentration-time curve (AUC) values increase linearly. Following repeated administration, steady state is achieved within 24 to 48 hours. Multiple-dose pharmacokinetics can be predicted from single-dose data.

The rate of pregabalin absorption is decreased when given with food, resulting in a decrease in Cmax of approximately 25% to 30% and an increase in Tmax to approximately 3 hours. However, administration of pregabalin with food has no clinically relevant effect on the total absorption of pregabalin. Therefore, pregabalin can be taken with or without food.

Pregabalin does not bind to plasma proteins. The apparent volume of distribution of pregabalin following oral administration is approximately 0.5 L/kg. Pregabalin is a substrate for system L transporter which is responsible for the transport of large amino acids across the blood brain barrier. Although there are no data in humans, pregabalin has been shown to cross the blood brain barrier in mice, rats, and monkeys. In addition, pregabalin has been shown to cross the placenta in rats and is present in the milk of lactating rats.

Metabolism and Elimination

Pregabalin undergoes negligible metabolism in humans. Following a dose of radiolabeled pregabalin, approximately 90% of the administered dose was recovered in the urine as unchanged pregabalin. The N-methylated derivative of pregabalin, the major metabolite of pregabalin found in urine, accounted for 0.9% of the dose. In preclinical studies, pregabalin (S‑enantiomer) did not undergo racemization to the R-enantiomer in mice, rats, rabbits, or monkeys.

Pregabalin is eliminated from the systemic circulation primarily by renal excretion as unchanged drug with a mean elimination half-life of 6.3 hours in subjects with normal renal function. Mean renal clearance was estimated to be 67.0 to 80.9 mL/min in young healthy subjects. Because pregabalin is not bound to plasma proteins this clearance rate indicates that renal tubular reabsorption is involved. Pregabalin elimination is nearly proportional to creatinine clearance (CLcr) [see Dosage and Administration (2.7)].

Pharmacokinetics in Specific Populations

Race

In population pharmacokinetic analyses of the clinical studies in various populations, the pharmacokinetics of LYRICA were not significantly affected by race (Caucasians, Blacks, and Hispanics).

Gender

Population pharmacokinetic analyses of the clinical studies showed that the relationship between daily dose and LYRICA drug exposure is similar between genders.

Renal Impairment and Hemodialysis

Pregabalin clearance is nearly proportional to creatinine clearance (CLcr). Dosage reduction in patients with renal dysfunction is necessary. Pregabalin is effectively removed from plasma by hemodialysis. Following a 4-hour hemodialysis treatment, plasma pregabalin concentrations are reduced by approximately 50%. For patients on hemodialysis, dosing must be modified [see Dosage and Administration (2.7)].

Elderly

Pregabalin oral clearance tended to decrease with increasing age. This decrease in pregabalin oral clearance is consistent with age-related decreases in CLcr. Reduction of pregabalin dose may be required in patients who have age-related compromised renal function [see Dosage and Administration (2.7)].

Pediatric Pharmacokinetics

Pediatric Patients (3 months to less than 17 years of age)

Pregabalin pharmacokinetics were evaluated in 358 pediatric patients 3 months to less than 17 years of age with partial‑onset seizures at dose levels of 2.5, 5, 10, and 15 mg/kg/day after single and multiple oral administration of pregabalin. Following oral administration, pregabalin reaches peak plasma concentration at 0.5 hours to 2 hours in the fasted state. Both apparent clearance (CL/F) and apparent volume of distribution increase as body weight increases. A weight-based dosing regimen is necessary to achieve pregabalin exposures in pediatric patients 1 month to less than 17 years of age similar to those observed in adults treated for partial‑onset seizures at effective doses [see Dosage and Administration (2.4)]. The mean t½ is 3 to 4 hours in pediatric subjects up to 6 years of age, and 4 to 6 hours in those 7 years of age and older. Pregabalin CL/F is nearly proportional to CLcr (mL/min). The relationship is similar in pediatric and adult subjects. When normalized per body weight, CL/F (mL/min/kg) in pediatric subjects weighing less than 30 kg is approximately 40% higher in comparison to subjects weighing greater than or equal to 30 kg [see Dosage and Administration (2.4)].

Drug Interactions

In Vitro Studies

Pregabalin, at concentrations that were, in general, 10-times those attained in clinical trials, does not inhibit human CYP1A2, CYP2A6, CYP2C9, CYP2C19, CYP2D6, CYP2E1, and CYP3A4 enzyme systems. In vitro drug interaction studies demonstrate that pregabalin does not induce CYP1A2 or CYP3A4 activity. Therefore, an increase in the metabolism of coadministered CYP1A2 substrates (e.g., theophylline, caffeine) or CYP3A4 substrates (e.g. midazolam, testosterone) is not anticipated.

In Vivo Studies

The drug interaction studies described in this section were conducted in healthy adults, and across various patient populations.

Gabapentin

The pharmacokinetic interactions of pregabalin and gabapentin were investigated in 12 healthy subjects following concomitant single-dose administration of 100-mg pregabalin and 300-mg gabapentin and in 18 healthy subjects following concomitant multiple-dose administration of 200-mg pregabalin every 8 hours and 400-mg gabapentin every 8 hours. Gabapentin pharmacokinetics following single- and multiple-dose administration were unaltered by pregabalin coadministration. The extent of pregabalin absorption was unaffected by gabapentin coadministration, although there was a small reduction in rate of absorption.

Oral Contraceptive

Pregabalin coadministration (200 mg three times a day) had no effect on the steady-state pharmacokinetics of norethindrone and ethinyl estradiol (1 mg/35 µg, respectively) in healthy subjects.

Lorazepam

Multiple-dose administration of pregabalin (300 mg twice a day) in healthy subjects had no effect on the rate and extent of lorazepam single-dose pharmacokinetics and single-dose administration of lorazepam (1 mg) had no effect on the steady-state pharmacokinetics of pregabalin.

Oxycodone

Multiple-dose administration of pregabalin (300 mg twice a day) in healthy subjects had no effect on the rate and extent of oxycodone single-dose pharmacokinetics. Single-dose administration of oxycodone (10 mg) had no effect on the steady-state pharmacokinetics of pregabalin.

Ethanol

Multiple-dose administration of pregabalin (300 mg twice a day) in healthy subjects had no effect on the rate and extent of ethanol single-dose pharmacokinetics and single-dose administration of ethanol (0.7 g/kg) had no effect on the steady-state pharmacokinetics of pregabalin.

Phenytoin, carbamazepine, valproic acid, and lamotrigine

Steady-state trough plasma concentrations of phenytoin, carbamazepine and carbamazepine 10,11 epoxide, valproic acid, and lamotrigine were not affected by concomitant pregabalin (200 mg three times a day) administration.

Population pharmacokinetic analyses in patients treated with pregabalin and various concomitant medications suggest the following:

Therapeutic class | Specific concomitant drug studied
Concomitant drug has no effect on the pharmacokinetics of pregabalin
Hypoglycemics | Glyburide, insulin, metformin
Diuretics | Furosemide
Antiepileptic Drugs | Tiagabine
Concomitant drug has no effect on the pharmacokinetics of pregabalin and pregabalin has no effect on the pharmacokinetics of concomitant drug
Antiepileptic Drugs | Carbamazepine, lamotrigine, phenobarbital, phenytoin, topiramate, valproic acid

13 NONCLINICAL TOXICOLOGY

13.1 Carcinogenesis, Mutagenesis, Impairment of Fertility

Carcinogenesis

A dose-dependent increase in the incidence of malignant vascular tumors (hemangiosarcomas) was observed in two strains of mice (B6C3F1 and CD-1) given pregabalin (200, 1000, or 5000 mg/kg) in the diet for two years. Plasma pregabalin exposure (AUC) in mice receiving the lowest dose that increased hemangiosarcomas was approximately equal to the human exposure at the maximum recommended dose (MRD) of 600 mg/day. A no-effect dose for induction of hemangiosarcomas in mice was not established. No evidence of carcinogenicity was seen in two studies in Wistar rats following dietary administration of pregabalin for two years at doses (50, 150, or 450 mg/kg in males and 100, 300, or 900 mg/kg in females) that were associated with plasma exposures in males and females up to approximately 14 and 24 times, respectively, human exposure at the MRD.

Mutagenesis

Pregabalin was not mutagenic in bacteria or in mammalian cells in vitro, was not clastogenic in mammalian systems in vitro and in vivo, and did not induce unscheduled DNA synthesis in mouse or rat hepatocytes.

Impairment of Fertility

In fertility studies in which male rats were orally administered pregabalin (50 to 2500 mg/kg) prior to and during mating with untreated females, a number of adverse reproductive and developmental effects were observed. These included decreased sperm counts and sperm motility, increased sperm abnormalities, reduced fertility, increased preimplantation embryo loss, decreased litter size, decreased fetal body weights, and an increased incidence of fetal abnormalities. Effects on sperm and fertility parameters were reversible in studies of this duration (3-4 months). The no-effect dose for male reproductive toxicity in these studies (100 mg/kg) was associated with a plasma pregabalin exposure (AUC) approximately 3 times human exposure at the maximum recommended dose (MRD) of 600 mg/day.

In addition, adverse reactions on reproductive organ (testes, epididymides) histopathology were observed in male rats exposed to pregabalin (500 to 1250 mg/kg) in general toxicology studies of four weeks or greater duration. The no-effect dose for male reproductive organ histopathology in rats (250 mg/kg) was associated with a plasma exposure approximately 8 times human exposure at the MRD.

In a fertility study in which female rats were given pregabalin (500, 1250, or 2500 mg/kg) orally prior to and during mating and early gestation, disrupted estrous cyclicity and an increased number of days to mating were seen at all doses, and embryolethality occurred at the highest dose. The low dose in this study produced a plasma exposure approximately 9 times that in humans receiving the MRD. A no-effect dose for female reproductive toxicity in rats was not established.

13.2 Animal Toxicology and/or Pharmacology

Dermatopathy

Skin lesions ranging from erythema to necrosis were seen in repeated-dose toxicology studies in both rats and monkeys. The etiology of these skin lesions is unknown. At the maximum recommended human dose (MRD) of 600 mg/day, there is a 2-fold safety margin for the dermatological lesions. The more severe dermatopathies involving necrosis were associated with pregabalin exposures (as expressed by plasma AUCs) of approximately 3 to 8 times those achieved in humans given the MRD. No increase in incidence of skin lesions was observed in clinical studies.

Ocular Lesions

Ocular lesions (characterized by retinal atrophy [including loss of photoreceptor cells] and/or corneal inflammation/mineralization) were observed in two lifetime carcinogenicity studies in Wistar rats. These findings were observed at plasma pregabalin exposures (AUC) greater than or equal to 2 times those achieved in humans given the maximum recommended dose of 600 mg/day. A no-effect dose for ocular lesions was not established. Similar lesions were not observed in lifetime carcinogenicity studies in two strains of mice or in monkeys treated for 1 year.

14 CLINICAL STUDIES

14.1 Neuropathic Pain Associated with Diabetic Peripheral Neuropathy

The efficacy of the maximum recommended dose of LYRICA for the management of neuropathic pain associated with diabetic peripheral neuropathy was established in three double‑blind, placebo-controlled, multicenter studies with three times a day dosing, two of which studied the maximum recommended dose. Patients were enrolled with either Type 1 or Type 2 diabetes mellitus and a diagnosis of painful distal symmetrical sensorimotor polyneuropathy for 1 to 5 years. A total of 89% of patients completed Studies DPN 1 and DPN 2. The patients had a minimum mean baseline pain score of greater than or equal to 4 on an 11-point numerical pain rating scale ranging from 0 (no pain) to 10 (worst possible pain). The baseline mean pain scores across the two studies ranged from 6.1 to 6.7. Patients were permitted up to 4 grams of acetaminophen per day as needed for pain, in addition to pregabalin. Patients recorded their pain daily in a diary.

Study DPN 1: This 5-week study compared LYRICA 25, 100, or 200 mg three times a day with placebo. Treatment with LYRICA 100 and 200 mg three times a day statistically significantly improved the endpoint mean pain score and increased the proportion of patients with at least a 50% reduction in pain score from baseline. There was no evidence of a greater effect on pain scores of the 200 mg three times a day dose than the 100 mg three times a day dose, but there was evidence of dose dependent adverse reactions [see Adverse Reactions (6.1)]. For a range of levels of improvement in pain intensity from baseline to study endpoint, Figure 1 shows the fraction of patients achieving that level of improvement. The figure is cumulative, so that patients whose change from baseline is, for example, 50%, are also included at every level of improvement below 50%. Patients who did not complete the study were assigned 0% improvement. Some patients experienced a decrease in pain as early as Week 1, which persisted throughout the study.

Figure 1: Patients Achieving Various Levels of Improvement in Pain Intensity – Study DPN 1

Study DPN 2: This 8-week study compared LYRICA 100 mg three times a day with placebo. Treatment with LYRICA 100 mg three times a day statistically significantly improved the endpoint mean pain score and increased the proportion of patients with at least a 50% reduction in pain score from baseline. For various levels of improvement in pain intensity from baseline to study endpoint, Figure 2 shows the fraction of patients achieving that level of improvement. The figure is cumulative, so that patients whose change from baseline is, for example, 50%, are also included at every level of improvement below 50%. Patients who did not complete the study were assigned 0% improvement. Some patients experienced a decrease in pain as early as Week 1, which persisted throughout the study.

Figure 2: Patients Achieving Various Levels of Improvement in Pain Intensity – Study DPN 2

14.2 Postherpetic Neuralgia

The efficacy of LYRICA for the management of postherpetic neuralgia was established in three double-blind, placebo-controlled, multicenter studies. These studies enrolled patients with neuralgia persisting for at least 3 months following healing of herpes zoster rash and a minimum baseline score of greater than or equal to 4 on an 11-point numerical pain rating scale ranging from 0 (no pain) to 10 (worst possible pain). Seventy-three percent of patients completed the studies. The baseline mean pain scores across the 3 studies ranged from 6 to 7. Patients were permitted up to 4 grams of acetaminophen per day as needed for pain, in addition to pregabalin. Patients recorded their pain daily in a diary.

Study PHN 1: This 13-week study compared LYRICA 75, 150, and 300 mg twice daily with placebo. Patients with creatinine clearance (CLcr) between 30 to 60 mL/min were randomized to 75 mg, 150 mg, or placebo twice daily. Patients with creatinine clearance greater than 60 mL/min were randomized to 75 mg, 150 mg, 300 mg or placebo twice daily. In patients with creatinine clearance greater than 60 mL/min treatment with all doses of LYRICA statistically significantly improved the endpoint mean pain score and increased the proportion of patients with at least a 50% reduction in pain score from baseline. Despite differences in dosing based on renal function, patients with creatinine clearance between 30 to 60 mL/min tolerated LYRICA less well than patients with creatinine clearance greater than 60 mL/min as evidenced by higher rates of discontinuation due to adverse reactions. For various levels of improvement in pain intensity from baseline to study endpoint, Figure 3 shows the fraction of patients achieving that level of improvement. The figure is cumulative, so that patients whose change from baseline is, for example, 50%, are also included at every level of improvement below 50%. Patients who did not complete the study were assigned 0% improvement. Some patients experienced a decrease in pain as early as Week 1, which persisted throughout the study.

Figure 3: Patients Achieving Various Levels of Improvement in Pain Intensity – Study PHN 1

Study PHN 2: This 8-week study compared LYRICA 100 or 200 mg three times a day with placebo, with doses assigned based on creatinine clearance. Patients with creatinine clearance between 30 to 60 mL/min were treated with 100 mg three times a day, and patients with creatinine clearance greater than 60 mL/min were treated with 200 mg three times daily. Treatment with LYRICA statistically significantly improved the endpoint mean pain score and increased the proportion of patients with at least a 50% reduction in pain score from baseline. For various levels of improvement in pain intensity from baseline to study endpoint, Figure 4 shows the fraction of patients achieving those levels of improvement. The figure is cumulative, so that patients whose change from baseline is, for example, 50%, are also included at every level of improvement below 50%. Patients who did not complete the study were assigned 0% improvement. Some patients experienced a decrease in pain as early as Week 1, which persisted throughout the study.

Figure 4: Patients Achieving Various Levels of Improvement in Pain Intensity – Study PHN 2

Study PHN 3: This 8-week study compared LYRICA 50 or 100 mg three times a day with placebo with doses assigned regardless of creatinine clearance. Treatment with LYRICA 50 and 100 mg three times a day statistically significantly improved the endpoint mean pain score and increased the proportion of patients with at least a 50% reduction in pain score from baseline. Patients with creatinine clearance between 30 to 60 mL/min tolerated LYRICA less well than patients with creatinine clearance greater than 60 mL/min as evidenced by markedly higher rates of discontinuation due to adverse reactions. For various levels of improvement in pain intensity from baseline to study endpoint, Figure 5 shows the fraction of patients achieving that level of improvement. The figure is cumulative, so that patients whose change from baseline is, for example, 50%, are also included at every level of improvement below 50%. Patients who did not complete the study were assigned 0% improvement. Some patients experienced a decrease in pain as early as Week 1, which persisted throughout the study.

Figure 5: Patients Achieving Various Levels of Improvement in Pain Intensity – Study PHN 3

14.3 Adjunctive Therapy for Partial-Onset Seizures in Patients 1 Month of Age and Older

Adjunctive Therapy for Partial-Onset Seizures in Adult Patients

The efficacy of LYRICA as adjunctive therapy for partial‑onset seizures in adult patients was established in three 12-week, randomized, double-blind, placebo-controlled, multicenter studies. Patients were enrolled who had partial‑onset seizures with or without secondary generalization and were not adequately controlled with 1 to 3 concomitant antiepileptic drugs (AEDs). Patients taking gabapentin were required to discontinue gabapentin treatment 1 week prior to entering baseline. During an 8-week baseline period, patients had to experience at least 6 partial‑onset seizures with no seizure-free period exceeding 4 weeks. The mean duration of epilepsy was 25 years in these 3 studies and the mean and median baseline seizure frequencies were 22.5 and 10 seizures per month, respectively. Approximately half of the patients were taking 2 concurrent AEDs at baseline. Among the LYRICA-treated patients, 80% completed the double-blind phase of the studies.

Table 11 shows median baseline seizure rates and median percent reduction in seizure frequency by dose.

Table 11. Seizure Response in Controlled, Adjunctive Epilepsy Studies in Adults
Daily Dose of Pregabalin | Dosing Regimen | N | Baseline Seizure Frequency/mo | Median % Change from Baseline | p-value, vs. placebo
Study E1
Placebo | BID | 100 | 9.5 | 0
50 mg/day | BID | 88 | 10.3 | -9 | 0.4230
150 mg/day | BID | 86 | 8.8 | -35 | 0.0001
300 mg/day | BID | 90 | 9.8 | -37 | 0.0001
600 mg/day | BID | 89 | 9.0 | -51 | 0.0001
Study E2
Placebo | TID | 96 | 9.3 | 1
150 mg/day | TID | 99 | 11.5 | -17 | 0.0007
600 mg/day | TID | 92 | 12.3 | -43 | 0.0001
Study E3
Placebo | BID/TID | 98 | 11 | -1
600 mg/day | BID | 103 | 9.5 | -36 | 0.0001
600 mg/day | TID | 111 | 10 | -48 | 0.0001

In the first study (E1), there was evidence of a dose-response relationship for total daily doses of LYRICA between 150 and 600 mg/day; a dose of 50 mg/day was not effective. In the first study (E1), each daily dose was divided into two equal doses (twice a day dosing). In the second study (E2), each daily dose was divided into three equal doses (three times a day dosing). In the third study (E3), the same total daily dose was divided into two equal doses for one group (twice a day dosing) and three equal doses for another group (three times a day dosing). While the three times a day dosing group in Study E3 performed numerically better than the twice a day dosing group, this difference was small and not statistically significant.

A secondary outcome measure included the responder rate (proportion of patients with greater than or equal to 50% reduction from baseline in partial seizure frequency). The following figure displays responder rate by dose for two of the studies.

Figure 6: Responder Rate by Adjunctive Epilepsy Study

Figure 7: Seizure Reduction by Dose (All Partial-Onset Seizures) for Studies E1, E2, and E3

Subset evaluations of the antiseizure efficacy of LYRICA showed no clinically important differences as a function of age, gender, or race.

Adjunctive Therapy for Partial-Onset Seizures in Pediatric Patients 4 to Less Than 17 Years of Age

The efficacy of LYRICA as adjunctive therapy in partial‑onset seizures was established in a 12‑week, randomized, double-blind, placebo-controlled, multicenter study in pediatric patients 4 years to less than 17 years of age with partial‑onset seizures with or without secondary generalization. During an 8-week baseline period, patients had to experience at least 6 partial‑onset seizures with no seizure-free period exceeding 4 weeks. The mean duration of epilepsy was 6 years and the mean and median baseline seizure frequencies were 57 and 18 seizures per month, respectively. Approximately 74% of the patients were taking 2 to 3 concurrent AEDs at baseline. Among the LYRICA-treated patients, 87% completed the double‑blind phase of the study.

In this study, LYRICA 2.5 mg/kg/day (maximum 150 mg/day) and 10 mg/kg/day (maximum 600 mg/day) were compared to placebo. Administration of each daily dose was divided into two equal doses (twice a day dosing). Because of higher weight-normalized clearance in patients with body weight less than 30 kg [see Clinical Pharmacology (12.3)], the LYRICA dose was increased by 40% to 3.5 mg/kg/day for patients weighing less than 30 kg randomized to the 2.5 mg/kg/day group or to 14 mg/kg/day for patients randomized to the 10 mg/kg/day group.

Table 12 shows median baseline seizure rates, median percent change from baseline in seizure rates, and percent difference relative to placebo (derived from the primary analysis model) by dose.

Table 12. Seizure Response in Controlled Adjunctive Partial‑Onset Seizure Study in Pediatric Patients 4 to Less Than 17 Years of Age
Daily Dose of LYRICA | N | Median Baseline Seizure Frequency/; 28 days | Median % Change from Baseline | % Difference Relative to Placebo | p-value, versus placebo
Placebo | 93 | 16.5 | -16.9 | Not applicable
2.5 mg/kg/day (BID) [2.5 mg/kg/day: Maximum dose 150 mg/day. Includes patients less than 30 kg for whom dose was adjusted to 3.5 mg/kg/day.] | 104 | 23.8 | -27.3 | -10.5 | 0.2577
10 mg/kg/day (BID) [10 mg/kg/day: Maximum dose 600 mg/day. Includes patients less than 30 kg for whom dose was adjusted to 14 mg/kg/day.] | 97 | 17.5 | -37.1 | -21.0 | 0.0185
Abbreviations: BID=twice daily; N=number.

There was evidence of a dose-response relationship for total daily doses of LYRICA between 2.5 mg/kg/day and 10 mg/kg/day. A significant improvement in seizure rate was observed for LYRICA 10 mg/kg/day group compared with placebo. While the 2.5 mg/kg/day group performed numerically better than placebo, this difference was not statistically significant.

A key secondary efficacy measure, the responder rate (proportion of patients with greater than or equal to 50% reduction from baseline in partial seizure frequency) showed improvements for LYRICA groups compared with placebo. The following figure displays responder rate by dose:

Figure 8: Responder Rate (Greater than or Equal to 50% Reduction)

Adjunctive Therapy for Partial-Onset Seizures in Pediatric Patients 1 Month to Less Than 4 Years of Age

The efficacy of LYRICA as adjunctive therapy in partial‑onset seizures was established in a 14‑day, randomized, double-blind, placebo-controlled, multicenter study in children 1 month to less than 4 years of age with partial‑onset seizures with or without secondary generalization. The youngest patient evaluated was 3 months of age. During a 48- to 72-hour baseline video electroencephalogram (EEG), patients had to experience at least 2 partial‑onset seizures. The mean duration of epilepsy at baseline was 1.6 years and the mean and median baseline seizure frequencies were 12.2 and 4.4 seizures per day, respectively. Approximately 33%, 50%, and 17% of patients were taking 1, 2, or 3 concurrent AEDs at baseline, respectively. Among the LYRICA-treated patients, 97% completed the double-blind phase of the study.

In this study, LYRICA 7 mg/kg/day and 14 mg/kg/day were compared to placebo. Administration of each daily dose was divided into three equal doses (three times a day dosing). The primary endpoint was the 24‑hour partial‑onset seizure rate based on the comparison of the baseline video EEG to a repeat 48‑72 hour video EEG performed at the end of 14 days of double‑blind treatment.

Table 13 shows median baseline seizure rates, median percent change from baseline in seizure rates, and percent difference relative to placebo (derived from the primary analysis model) by dose.

Table 13. Seizure Response in Controlled Adjunctive Partial‑Onset Seizure Study in Pediatric Patients 1 Month to Less Than 4 Years of Age
Daily Dose of LYRICA | N | Median Baseline Seizure Frequency/; 24 hours | Median % Change from Baseline | % Difference Relative to Placebo | p-value, versus placebo
Placebo | 53 | 2.9 | 22.2 | Not applicable
7 mg/kg/day | 59 | 4.7 | 16.8 | 15.1 | 0.4606
14 mg/kg/day | 28 | 5.4 | 70.0 | -43.9 | 0.0223
Abbreviations: N=number of patients

A significant improvement in partial‑onset seizure rate was observed for LYRICA 14 mg/kg/day group compared with placebo. Patients treated with LYRICA 7 mg/kg/day did not show improvement relative to placebo.

Responder rates (≥50% or greater reduction in partial‑onset seizure frequency) were a secondary efficacy parameter; patients treated with LYRICA 14 mg/kg/day showed numerical improvement compared with placebo, while patients treated with LYRICA 7 mg/kg/day did not show improvement relative to placebo: the responder rates were 53.6%, 30.5%, and 41.5% for LYRICA 14 mg/kg/day, LYRICA 7 mg/kg/day, and placebo, respectively.

14.4 Management of Fibromyalgia

The efficacy of LYRICA for management of fibromyalgia was established in one 14-week, double-blind, placebo-controlled, multicenter study (F1) and one six-month, randomized withdrawal study (F2). Studies F1 and F2 enrolled patients with a diagnosis of fibromyalgia using the American College of Rheumatology (ACR) criteria (history of widespread pain for 3 months, and pain present at 11 or more of the 18 specific tender point sites). The studies showed a reduction in pain by visual analog scale. In addition, improvement was demonstrated based on a patient global assessment (PGIC), and on the Fibromyalgia Impact Questionnaire (FIQ).

Study F1: This 14-week study compared LYRICA total daily doses of 300 mg, 450 mg and 600 mg with placebo. Patients were enrolled with a minimum mean baseline pain score of greater than or equal to 4 on an 11-point numeric pain rating scale and a score of greater than or equal to 40 mm on the 100 mm pain visual analog scale (VAS). The baseline mean pain score in this trial was 6.7. Responders to placebo in an initial one-week run-in phase were not randomized into subsequent phases of the study. A total of 64% of patients randomized to LYRICA completed the study. There was no evidence of a greater effect on pain scores of the 600 mg daily dose than the 450 mg daily dose, but there was evidence of dose-dependent adverse reactions [see Adverse Reactions (6.1)]. Some patients experienced a decrease in pain as early as Week 1, which persisted throughout the study. The results are summarized in Figure 9 and Table 14.

For various levels of improvement in pain intensity from baseline to study endpoint, Figure 9 shows the fraction of patients achieving that level of improvement. The figure is cumulative. Patients who did not complete the study were assigned 0% improvement. Some patients experienced a decrease in pain as early as Week 1, which persisted throughout the study.

Figure 9: Patients Achieving Various Levels of Improvement in Pain Intensity – Fibromyalgia Study F1

Table 14. Patient Global Response in Fibromyalgia Study F1
Patient Global Impression of Change
Treatment Group (mg/day) | % Any Improvement | 95% CI
Placebo | 47.6 | (40.0,55.2)
PGB 300 | 68.1 | (60.9, 75.3)
PGB 450 | 77.8 | (71.5, 84.0)
PGB 600 | 66.1 | (59.1, 73.1)
PGB = Pregabalin

Study F2: This randomized withdrawal study compared LYRICA with placebo. Patients were titrated during a 6-week open-label dose optimization phase to a total daily dose of 300 mg, 450 mg, or 600 mg. Patients were considered to be responders if they had both: 1) at least a 50% reduction in pain (VAS) and, 2) rated their overall improvement on the PGIC as “much improved” or “very much improved.” Those who responded to treatment were then randomized in the double-blind treatment phase to either the dose achieved in the open-label phase or to placebo. Patients were treated for up to 6 months following randomization. Efficacy was assessed by time to loss of therapeutic response, defined as 1) less than 30% reduction in pain (VAS) from open-label baseline during two consecutive visits of the double-blind phase, or 2) worsening of FM symptoms necessitating an alternative treatment. Fifty-four percent of patients were able to titrate to an effective and tolerable dose of LYRICA during the 6-week open-label phase. Of the patients entering the randomized treatment phase assigned to remain on LYRICA, 38% of patients completed 26 weeks of treatment versus 19% of placebo-treated patients.

When considering return of pain or withdrawal due to adverse events as loss of response (LTR), treatment with LYRICA resulted in a longer time to loss of therapeutic response than treatment with placebo. Fifty-three percent of the pregabalin-treated subjects compared to 33% of placebo patients remained on study drug and maintained a therapeutic response to Week 26 of the study. Treatment with LYRICA also resulted in a longer time to loss of response based on the FIQ^1, and longer time to loss of overall assessment of patient status, as measured by the PGIC^2.

^1 Time to worsening of the FIQ was defined as the time to a 1-point increase from double-blind baseline in each of the subscales, and a 5-point increase from double-blind baseline evaluation for the FIQ total score.

^2 Time to PGIC lack of improvement was defined as time to PGIC assessments indicating less improvement than “much improvement.”

Figure 10: Time to Loss of Therapeutic Response, Fibromyalgia Study F2 (Kaplan-Meier Analysis)

14.5 Management of Neuropathic Pain Associated with Spinal Cord Injury

The efficacy of LYRICA for the management of neuropathic pain associated with spinal cord injury was established in two double-blind, placebo-controlled, multicenter studies. Patients were enrolled with neuropathic pain associated with spinal cord injury that persisted continuously for at least three months or with relapses and remissions for at least six months. A total of 63% of patients completed study 1 and 84% completed study 2. The patients had a minimum mean baseline pain score of greater than or equal to 4 on an 11-point numerical pain rating scale ranging from 0 (no pain) to 10 (worst possible pain). The baseline mean pain scores across the two studies ranged from 6.5 to 6.7.

Patients were allowed to take opioids, non-opioid analgesics, antiepileptic drugs, muscle relaxants, and antidepressant drugs if the dose was stable for 30 days prior to screening. Patients were allowed to take acetaminophen and nonsteroidal anti-inflammatory drugs during the studies.

Study SCI 1: This 12-week, randomized, double-blind, parallel-group, multicenter, flexible dose (150-600 mg/day) study compared pregabalin with placebo. The 12-week study consisted of a 3‑week dose adjustment phase and a 9-week dose maintenance phase. Treatment with LYRICA 150-600 mg/day statistically significantly improved the endpoint weekly mean pain score, and increased the proportion of patients with at least a 30% and 50% reduction in pain score from baseline. The fraction of patients achieving various levels of improvement in pain intensity from baseline to Week 12 is presented in Figure 11. Some patients experienced a decrease in pain as early as week 1, which persisted throughout the study.

Figure 11: Patients Achieving Various Levels of Improvement in Pain Intensity – Study SCI 1

Study SCI 2: This 16-week, randomized, double-blind, placebo-controlled, parallel-group, multicenter, flexible dose (150-600 mg/day, in increments of 150 mg) study compared the efficacy, safety and tolerability of pregabalin with placebo. The 16-week study consisted of a 4‑week dose adjustment phase and a 12-week dose maintenance phase. Treatment with LYRICA statistically significantly improved the endpoint weekly mean pain score, and increased the proportion of patients with at least a 30% and 50% reduction in pain score from baseline. The fraction of patients achieving various levels of improvement in pain intensity from baseline to Week 16 is presented in Figure 12. Some patients experienced a decrease in pain as early as week 1, which persisted throughout the study.

Figure 12: Patients Achieving Various Levels of Improvement in Pain Intensity – Study SCI 2

16 HOW SUPPLIED/STORAGE AND HANDLING

25 mg capsules:

White, hard-gelatin capsule printed with black ink “VTRS” on the cap, “PGN” over “25” on the body; available in:

Bottles of 90: NDC 58151-236-77

50 mg capsules:

White, hard-gelatin capsule printed with black ink “VTRS” on the cap, “PGN” over “50” and an ink band on the body, available in:

Bottles of 90: NDC 58151-237-77

Unit-Dose Blister Packages of 100: NDC 58151-237-88

75 mg capsules:

White/orange hard gelatin capsule printed with black ink “VTRS” on the cap, “PGN” over “75” on the body; available in:

Bottles of 90: NDC 58151-238-77

Unit-Dose Blister Packages of 100: NDC 58151-238-88

100 mg capsules:

Orange, hard-gelatin capsule printed with black ink “VTRS” on the cap, “PGN” over “100” on the body, available in:

Bottles of 90: NDC 58151-239-77

Unit-Dose Blister Packages of 100: NDC 58151-239-88

150 mg capsules:

White hard gelatin capsule printed with black ink “VTRS” on the cap, “PGN” over “150” on the body, available in:

Bottles of 90: NDC 58151-240-77

Unit-Dose Blister Packages of 100: NDC 58151-240-88

200 mg capsules:

Light orange hard gelatin capsule printed with black ink “VTRS” on the cap, “PGN” over “200” on the body, available in:

Bottles of 90: NDC 58151-241-77

225 mg capsules:

White/light orange hard gelatin capsule printed with black ink “VTRS” on the cap, “PGN” over “225” on the body; available in:

Bottles of 90: NDC 58151-243-77

300 mg capsules:

White/orange hard gelatin capsule printed with black ink “VTRS” on the cap, “PGN” over “300” on the body, available in:

Bottles of 90: NDC 58151-242-77

20 mg/mL oral solution:

16 fluid ounce white high density polyethylene (HDPE) bottle with a polyethylene-lined closure:

16 fluid ounce bottle NDC 58151-244-35

Storage and Handling

Store at 25°C (77°F); excursions permitted to 15°C to 30°C (59°F to 86°F) (see USP Controlled Room Temperature).

17 PATIENT COUNSELING INFORMATION

Advise the patient to read the FDA‑approved patient labeling (Medication Guide).

Angioedema

Advise patients that LYRICA may cause angioedema, with swelling of the face, mouth (lip, gum, tongue) and neck (larynx and pharynx) that can lead to life-threatening respiratory compromise. Instruct patients to discontinue LYRICA and immediately seek medical care if they experience these symptoms [see Warnings and Precautions (5.1)].

Hypersensitivity

Advise patients that LYRICA has been associated with hypersensitivity reactions such as wheezing, dyspnea, rash, hives, and blisters. Instruct patients to discontinue LYRICA and immediately seek medical care if they experience these symptoms [see Warnings and Precautions (5.2)].

Suicidal Thinking and Behavior

Counsel patients, their caregivers, and families that AEDs, including LYRICA, may increase the risk of suicidal thoughts and behavior and should be advised of the need to be alert for the emergence or worsening of symptoms of depression, any unusual changes in mood or behavior, or the emergence of suicidal thoughts, behavior, or thoughts about self-harm. Instruct patients, caregivers, and families to report behaviors of concern immediately to healthcare providers. Also inform patients who plan to or have discontinued LYRICA that suicidal thoughts and behavior can appear even after the drug is stopped [see Warnings and Precautions (5.3)].

Respiratory Depression

Inform patients about the risk of respiratory depression. Include information that the risk is greatest for those using concomitant central nervous system (CNS) depressants (such as opioid analgesics) or in those with underlying respiratory impairment. Teach patients how to recognize respiratory depression and advise them to seek medical attention immediately if it occurs [see Warnings and Precautions (5.5)].

Dizziness and Somnolence

Counsel patients that LYRICA may cause dizziness, somnolence, blurred vision and other CNS signs and symptoms. Accordingly, advise patients not to drive, operate complex machinery, or engage in other hazardous activities until they have gained sufficient experience on LYRICA to gauge whether or not it affects their mental, visual, and/or motor performance adversely [see Warnings and Precautions (5.6)].

CNS Depressants

Inform patients who require concomitant treatment with central nervous system depressants such as opiates or benzodiazepines that they may experience additive CNS side effects, such as respiratory depression, somnolence, and dizziness [see Warnings and Precautions (5.5, 5.6) and Drug Interactions (7)]. Advise patients to avoid consuming alcohol while taking LYRICA, as LYRICA may potentiate the impairment of motor skills and sedating effects of alcohol.

Adverse Reactions with Abrupt or Rapid Discontinuation

Advise patients to take LYRICA as prescribed. Abrupt or rapid discontinuation may result in increased seizure frequency in patients with seizure disorders, and insomnia, nausea, headache, anxiety, hyperhidrosis, or diarrhea [see Warnings and Precautions (5.4)].

Missed Dose

Counsel patients if they miss a dose, they should take it as soon as they remember. If it is almost time for the next dose, they should skip the missed dose and take the next dose at their regularly scheduled time. Instruct patients not to take two doses at the same time.

Weight Gain and Edema

Counsel patients that LYRICA may cause edema and weight gain. Advise patients that concomitant treatment with LYRICA and a thiazolidinedione antidiabetic agent may lead to an additive effect on edema and weight gain. For patients with preexisting cardiac conditions, this may increase the risk of heart failure [see Warnings and Precautions (5.7, 5.8)].

Ophthalmological Effects

Counsel patients that LYRICA may cause visual disturbances. Inform patients that if changes in vision occur, they should notify their physician [see Warnings and Precautions (5.10)].

Creatine Kinase Elevations

Instruct patients to promptly report unexplained muscle pain, tenderness, or weakness, particularly if accompanied by malaise or fever [see Warnings and Precautions (5.11)].

Use in Pregnancy

Instruct patients to inform their healthcare provider if they are pregnant or intend to become pregnant during therapy, and to notify their physician if they are breast feeding or intend to breast feed during therapy [see Use in Specific Populations (8.1) and (8.2)].

Encourage patients to enroll in the North American Antiepileptic Drug (NAAED) Pregnancy Registry if they become pregnant. This registry is collecting information about the safety of antiepileptic drugs during pregnancy. To enroll, patients can call the toll-free number 1-888-233-2334 [see Use in Specific Populations (8.1)].

Lactation

Advise nursing mothers that breastfeeding is not recommended during treatment with LYRICA [see Use in Specific Populations (8.2)].

Male Fertility

Inform men being treated with LYRICA who plan to father a child of the potential risk of male‑mediated teratogenicity. In preclinical studies in rats, pregabalin was associated with an increased risk of male-mediated teratogenicity. The clinical significance of this finding is uncertain [see Nonclinical Toxicology (13.1) and Use in Specific Populations (8.3)].

Dermatopathy

Instruct diabetic patients to pay particular attention to skin integrity while being treated with LYRICA and to inform their healthcare provider about any sores or skin problems. Some animals treated with pregabalin developed skin ulcerations, although no increased incidence of skin lesions associated with LYRICA was observed in clinical trials [see Nonclinical Toxicology (13.2)].

Distributed by:
Viatris Specialty LLC
Morgantown, WV 26505 U.S.A.

© 2025 Viatris Inc.

LYRICA is a registered trademark of Viatris Specialty LLC, a Viatris Company.

The brands listed are trademarks of their respective owners.

UPJ:LYRCCOS:R2

MEDICATION GUIDE

LYRICA (LEER-i-kah)

(pregabalin)

Capsules, CV

LYRICA (LEER-i-kah)

(pregabalin)

Oral Solution, CV

Read this Medication Guide before you start taking LYRICA and each time you get a refill. There may be new information. This information does not take the place of talking to your healthcare provider about your medical condition or treatment. If you have any questions about LYRICA, ask your healthcare provider or pharmacist.

What is the most important information I should know about LYRICA?

LYRICA may cause serious side effects including:

- serious, even life-threatening, allergic reactions
- suicidal thoughts or actions
- serious breathing problems

- swelling of your hands, legs and feet
- dizziness and sleepiness

These serious side effects are described below:

- Serious, even life-threatening, allergic reactions.
  Stop taking LYRICA and call your healthcare provider right away if you have any of these signs of a serious allergic reaction:
  - swelling of your face, mouth, lips, gums, tongue, throat or neck
  - trouble breathing
  - rash, hives (raised bumps) or blisters
- Like other antiepileptic drugs, LYRICA may cause suicidal thoughts or actions in a very small number of people, about 1 in 500. This can happen while you take LYRICA or after stopping. Call a healthcare provider right away if you have any of these symptoms, especially if they are new, worse, or worry you:

- thoughts about suicide or dying
- attempts to commit suicide
- new or worse depression
- new or worse anxiety
- feeling agitated or restless
- panic attacks

- trouble sleeping (insomnia)
- new or worse irritability
- acting aggressive, being angry, or violent
- acting on dangerous impulses
- an extreme increase in activity and talking (mania)
- other unusual changes in behavior or mood

If you have suicidal thoughts or actions, do not stop LYRICA without first talking to a healthcare provider.
2. Stopping LYRICA suddenly can cause serious problems.
3. Suicidal thoughts or actions can be caused by things other than medicines. If you have suicidal thoughts or actions, your healthcare provider may check for other causes.
How can I watch for early symptoms of suicidal thoughts and actions?
5. Pay attention to any changes, especially sudden changes, in mood, behaviors, thoughts, or feelings.
6. Keep all follow-up visits with your healthcare provider as scheduled.
7. Call your healthcare provider between visits as needed, especially if you are worried about symptoms.
8. Serious breathing problems can occur when LYRICA is taken with other medicines that can cause severe sleepiness or decreased awareness, or when it is taken by someone who already has breathing problems. Watch for increased sleepiness or decreased breathing when starting LYRICA or when the dose is increased. Get help right away if breathing problems occur.
9. Swelling of your hands, legs and feet. This swelling can be a serious problem for people with heart problems.
10. Dizziness and sleepiness. Do not drive a car, work with machines, or do other dangerous activities until you know how LYRICA affects you. Ask your healthcare provider about when it will be okay to do these activities.

What is LYRICA?

LYRICA is a prescription medicine used in adults, 18 years of age and older to treat:

- pain from damaged nerves (neuropathic pain) that happens with diabetes
- pain from damaged nerves (neuropathic pain) that follows healing of shingles
- fibromyalgia (pain all over your body)
- pain from damaged nerves (neuropathic pain) that follows spinal cord injury

It is not known if LYRICA is safe and effective in people under 18 years of age for the treatment of fibromyalgia and neuropathic pain with diabetes, shingles, or spinal cord injury.

LYRICA is a prescription medicine used in people 1 month of age and older to treat:

- partial‑onset seizures when taken together with other seizure medicines.

For the treatment of partial‑onset seizures when taken together with other seizure medicines, it is not known if LYRICA is safe and effective in children under 1 month of age.

Who should not take LYRICA?

Do not take LYRICA if you are allergic to pregabalin or any of the ingredients in LYRICA.

See “What is the most important information I should know about LYRICA?” for the signs of an allergic reaction.

See the end of this Medication Guide for a complete list of ingredients in LYRICA.

What should I tell my healthcare provider before taking LYRICA?

Before taking LYRICA, tell your healthcare provider about all your medical conditions, including if you:

- have or have had depression, mood problems or suicidal thoughts or behavior.
- have breathing problems.
- have kidney problems or get kidney dialysis.
- have heart problems including heart failure.
- have a bleeding problem or a low blood platelet count.
- have abused prescription medicines, street drugs, or alcohol in the past.
- have ever had swelling of your face, mouth, tongue, lips, gums, neck, or throat (angioedema).
- plan to father a child. Animal studies have shown that pregabalin, the active ingredient in LYRICA, made male animals less fertile and caused sperm to change. Also, in animal studies, birth defects were seen in the offspring (babies) of male animals treated with pregabalin. It is not known if these problems can happen in people who take LYRICA.
- are pregnant or plan to become pregnant. LYRICA may harm your unborn baby. You and your healthcare provider will decide if you should take LYRICA while you are pregnant.
  - If you become pregnant while taking LYRICA, talk to your healthcare provider about registering with the North American Antiepileptic Drug Pregnancy Registry. You can enroll in this registry by calling 1-888-233-2334. The purpose of this registry is to collect information about the safety of antiepileptic drugs during pregnancy. Information about the registry can also be found at the website, http://www.aedpregnancyregistry.org/.
- are breastfeeding or plan to breastfeed. LYRICA passes into your breast milk. It is not known if LYRICA can harm your baby. Talk to your healthcare provider about the best way to feed your baby if you take LYRICA. Breastfeeding is not recommended while taking LYRICA.

Tell your healthcare provider about all the medicines you take, including prescription and over-the-counter medicines, vitamins or herbal supplements. LYRICA and other medicines may affect each other causing side effects. Especially tell your healthcare provider if you take:

- angiotensin converting enzyme (ACE) inhibitors, which are used to treat many conditions, including high blood pressure. You may have a higher chance for swelling and hives if these medicines are taken with LYRICA.
- Avandia® (rosiglitazone) or Actos® (pioglitazone) for diabetes. You may have a higher chance of weight gain or swelling of your hands or feet if these medicines are taken with LYRICA.
- any opioid pain medicine (such as oxycodone), or medicines for anxiety (such as lorazepam) or insomnia (such as zolpidem). You may have a higher chance for dizziness, sleepiness or serious breathing problems if these medicines are taken with LYRICA.
- any medicines that make you sleepy.

Know the medicines you take. Keep a list of them with you to show your healthcare provider and pharmacist each time you get a new medicine. Do not start a new medicine without talking with your healthcare provider.

How should I take LYRICA?

- Take LYRICA exactly as prescribed. Your healthcare provider will tell you how much LYRICA to take and when to take it.
- LYRICA may be taken with or without food.
- Your healthcare provider may change your dose. Do not change your dose without talking to your healthcare provider.
- Do not stop taking LYRICA without talking to your healthcare provider. If you stop taking LYRICA suddenly you may have headaches, nausea, diarrhea, trouble sleeping, increased sweating, or you may feel anxious. If you have epilepsy and you stop taking LYRICA suddenly, you may have seizures more often. Talk with your healthcare provider about how to stop LYRICA slowly.
- If you miss a dose, take it as soon as you remember. If it is almost time for your next dose, just skip the missed dose. Take the next dose at your regular time. Do not take 2 doses at the same time.
- If you take too much LYRICA, call your healthcare provider or poison control center, or go to the nearest emergency room right away.

What should I avoid while taking LYRICA?

- Do not drive a car, work with machines, or do other dangerous activities until you know how LYRICA affects you.
- Do not drink alcohol while taking LYRICA. LYRICA and alcohol can affect each other and increase side effects such as sleepiness and dizziness.

What are the possible side effects of LYRICA?

LYRICA may cause serious side effects, including:

- See “What is the most important information I should know about LYRICA?"
- Muscle problems, muscle pain, soreness, or weakness. If you have these symptoms, especially if you feel sick and have a fever, tell your healthcare provider right away.
- Problems with your eyesight, including blurry vision. Call your healthcare provider if you have any changes in your eyesight.
- Weight gain. If you have diabetes, weight gain may affect the management of your diabetes. Weight gain can also be a serious problem for people with heart problems.
- Feeling “high”.

The most common side effects of LYRICA in adults are:

- dizziness
- blurry vision
- dry mouth

- weight gain
- sleepiness

- trouble concentrating
- swelling of hands and feet

The most common side effects of LYRICA in children are weight gain, increase in appetite, and sleepiness.

LYRICA caused skin sores in animal studies. Skin sores did not happen in studies in people. If you have diabetes, you should pay attention to your skin while taking LYRICA and tell your healthcare provider about any sores or skin problems.

Tell your healthcare provider about any side effect that bothers you or that does not go away.

These are not all the possible side effects of LYRICA. For more information, ask your healthcare provider or pharmacist.

Call your doctor for medical advice about side effects. You may report side effects to FDA at 1-800-FDA-1088.

How should I store LYRICA?

- Store LYRICA capsules and oral solution at room temperature between 68°F to 77°F (20°C to 25°C) in its original package.
- Safely throw away any LYRICA that is out of date or no longer needed.

Keep LYRICA and all medicines out of the reach of children.

General information about the safe and effective use of LYRICA

Medicines are sometimes prescribed for purposes other than those listed in a Medication Guide. Do not use LYRICA for a condition for which it was not prescribed. Do not give LYRICA to other people, even if they have the same symptoms you have. It may harm them. You can ask your healthcare provider or pharmacist for information about LYRICA that is written for health professionals.

What are the ingredients in LYRICA?

Active ingredient: pregabalin

Inactive ingredients:

LYRICA capsules: cornstarch, lactose monohydrate, talc

Capsule shell: gelatin and titanium dioxide; Orange capsule shell: red iron oxide; White capsule shell: colloidal silicon dioxide, sodium lauryl sulfate. Colloidal silicon dioxide is a manufacturing aid that may or may not be present in the capsule shells.

Imprinting ink: black iron oxide, potassium hydroxide, propylene glycol, shellac.

LYRICA oral solution: artificial strawberry #11545, dibasic sodium phosphate anhydrous, methylparaben, monobasic sodium phosphate anhydrous, propylparaben, purified water, and sucralose.

Distributed by:
Viatris Specialty LLC
Morgantown, WV 26505 U.S.A.

© 2025 Viatris Inc.

LYRICA is a registered trademark of Viatris Specialty LLC, a Viatris Company.

The brands listed are trademarks of their respective owners.

UPJ:MG:LYRCCOS:R2

You can also call Viatris at 1-877-446-3679 (1-877-4-INFO-RX).

This Medication Guide has been approved by the U.S. Food and Drug Administration. Revised: 04/2025

PRINCIPAL DISPLAY PANEL – 25 mg

ALWAYS DISPENSE WITH MEDICATION GUIDE

NDC 58151-236-77

Lyrica® CV
(pregabalin)
capsules
25 mg

90 Capsules Rx only

Store at 25°C (77°F);
excursions permitted to
15°C to 30°C (59°F to 86°F)
[see USP Controlled Room
Temperature].

Dispense in tight (USP),
child-resistant containers.

DOSAGE AND USE
See accompanying
prescribing information.

Each capsule contains
25 mg pregabalin.

Distributed by:
Viatris Specialty LLC
Morgantown, WV 26505 U.S.A.

© 2023 Viatris Inc.

RUPJ236MM

PRINCIPAL DISPLAY PANEL – 50 mg

ALWAYS DISPENSE WITH MEDICATION GUIDE

NDC 58151-237-77

Lyrica® CV
(pregabalin)
capsules
50 mg

90 Capsules Rx only

Store at 25°C (77°F);
excursions permitted to
15°C to 30°C (59°F to 86°F)
[see USP Controlled Room
Temperature].

Dispense in tight (USP),
child-resistant containers.

DOSAGE AND USE
See accompanying
prescribing information.

Each capsule contains
50 mg pregabalin.

Distributed by:
Viatris Specialty LLC
Morgantown, WV 26505 U.S.A.

© 2023 Viatris Inc.

RUPJ237MM

PRINCIPAL DISPLAY PANEL – 75 mg

ALWAYS DISPENSE WITH MEDICATION GUIDE

NDC 58151-238-77

Lyrica® CV
(pregabalin)
capsules
75 mg

90 Capsules Rx only

Store at 25°C (77°F);
excursions permitted to
15°C to 30°C (59°F to 86°F)
[see USP Controlled Room
Temperature].

Dispense in tight (USP),
child-resistant containers.

DOSAGE AND USE
See accompanying
prescribing information.

Each capsule contains
75 mg pregabalin.

Distributed by:
Viatris Specialty LLC
Morgantown, WV 26505 U.S.A.

© 2023 Viatris Inc.

RUPJ238MM

PRINCIPAL DISPLAY PANEL – 100 mg

ALWAYS DISPENSE WITH MEDICATION GUIDE

NDC 58151-239-77

Lyrica® CV
(pregabalin)
capsules
100 mg

90 Capsules Rx only

Store at 25°C (77°F);
excursions permitted to
15°C to 30°C (59°F to 86°F)
[see USP Controlled Room
Temperature].

Dispense in tight (USP),
child-resistant containers.

DOSAGE AND USE
See accompanying
prescribing information.

Each capsule contains
100 mg pregabalin.

Distributed by:
Viatris Specialty LLC
Morgantown, WV 26505 U.S.A.

© 2023 Viatris Inc.

RUPJ239MM

PRINCIPAL DISPLAY PANEL – 150 mg

ALWAYS DISPENSE WITH MEDICATION GUIDE

NDC 58151-240-77

Lyrica® CV
(pregabalin)
capsules
150 mg

90 Capsules Rx only

Store at 25°C (77°F); excursions
permitted to 15°C to 30°C
(59°F to 86°F)
[see USP Controlled Room
Temperature].

Dispense in tight (USP),
child-resistant containers.

DOSAGE AND USE
See accompanying prescribing information.

Each capsule contains 150 mg pregabalin.

Distributed by:
Viatris Specialty LLC
Morgantown, WV 26505 U.S.A.

© 2023 Viatris Inc.

RUPJ240MM

PRINCIPAL DISPLAY PANEL – 200 mg

ALWAYS DISPENSE WITH MEDICATION GUIDE

NDC 58151-241-77

Lyrica® CV
(pregabalin)
capsules
200 mg

90 Capsules Rx only

Store at 25°C (77°F); excursions
permitted to 15°C to 30°C
(59°F to 86°F)
[see USP Controlled Room
Temperature].

Dispense in tight (USP),
child-resistant containers.

DOSAGE AND USE
See accompanying prescribing information.

Each capsule contains 200 mg pregabalin.

Distributed by:
Viatris Specialty LLC
Morgantown, WV 26505 U.S.A.

© 2023 Viatris Inc.

RUPJ241MM

PRINCIPAL DISPLAY PANEL – 225 mg

ALWAYS DISPENSE WITH MEDICATION GUIDE

NDC 58151-243-77

Lyrica® CV
(pregabalin)
capsules
225 mg

90 Capsules Rx only

Store at 25°C (77°F); excursions
permitted to 15°C to 30°C
(59°F to 86°F)
[see USP Controlled Room
Temperature].

Dispense in tight (USP),
child-resistant containers.

DOSAGE AND USE
See accompanying prescribing information.

Each capsule contains 225 mg pregabalin.

Distributed by:
Viatris Specialty LLC
Morgantown, WV 26505 U.S.A.

© 2023 Viatris Inc.

RUPJ243MM

PRINCIPAL DISPLAY PANEL – 300 mg

ALWAYS DISPENSE WITH MEDICATION GUIDE

NDC 58151-242-77

Lyrica® CV
(pregabalin)
capsules
300 mg

90 Capsules Rx only

Store at 25°C (77°F); excursions
permitted to 15°C to 30°C
(59°F to 86°F)
[see USP Controlled Room
Temperature].

Dispense in tight (USP),
child-resistant containers.

DOSAGE AND USE
See accompanying prescribing
information.

Each capsule contains 300 mg
pregabalin.

Distributed by:
Viatris Specialty LLC
Morgantown, WV 26505 U.S.A.

© 2023 Viatris Inc.

RUPJ242MM

PRINCIPAL DISPLAY PANEL – 20 mg per mL

ALWAYS DISPENSE WITH MEDICATION GUIDE

NDC 58151-244-35

Lyrica® CV
(pregabalin)
20 mg per mL
oral solution

FOR ORAL USE ONLY

16 fl oz (473 mL)

Rx only

Store at 25°C (77°F); excursions
permitted to 15°C to 30°C (59°F to 86°F)
[see USP Controlled Room
Temperature].

Dispense in tight (USP),
child-resistant containers.

Usual Dosage: See package insert for
dosage information.

Each mL contains 20 mg of pregabalin.

Distributed by:
Viatris Specialty LLC
Morgantown, WV 26505 U.S.A.

© 2023 Viatris Inc.

LYRICA is a registered trademark of

Viatris Specialty LLC, a Viatris Company.

UPJ:244:1C:R1